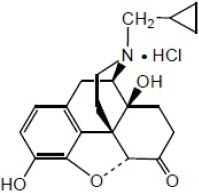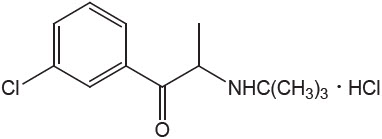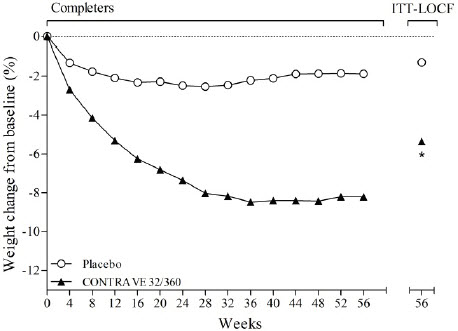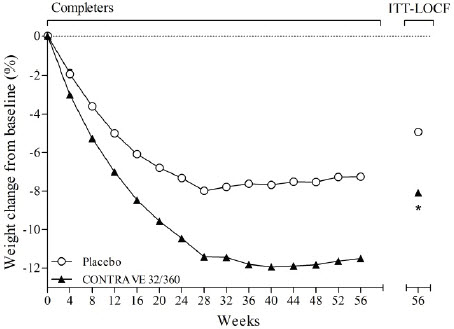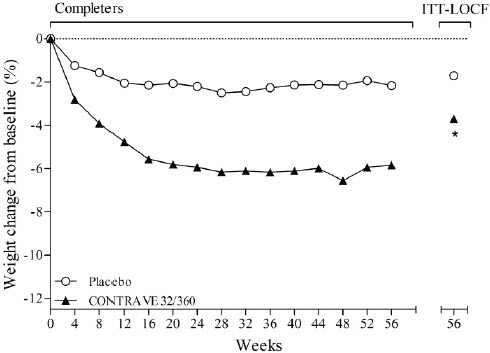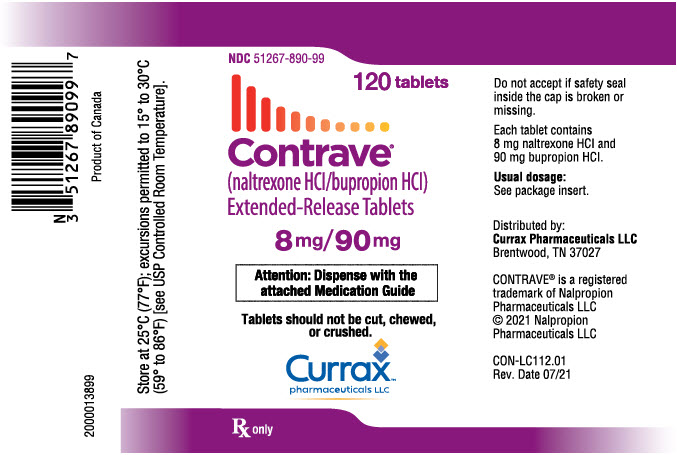 DRUG LABEL: Contrave
NDC: 51267-890 | Form: TABLET, EXTENDED RELEASE
Manufacturer: Nalpropion Pharmaceuticals LLC
Category: prescription | Type: HUMAN PRESCRIPTION DRUG LABEL
Date: 20251110

ACTIVE INGREDIENTS: NALTREXONE HYDROCHLORIDE 8 mg/1 1; BUPROPION HYDROCHLORIDE 90 mg/1 1
INACTIVE INGREDIENTS: MICROCRYSTALLINE CELLULOSE; HYDROXYPROPYL CELLULOSE (1600000 WAMW); ANHYDROUS LACTOSE; FD&C BLUE NO. 2; CYSTEINE HYDROCHLORIDE; CROSPOVIDONE (120 .MU.M); MAGNESIUM STEARATE; HYPROMELLOSE, UNSPECIFIED; EDETATE DISODIUM; LACTOSE MONOHYDRATE; SILICON DIOXIDE

HIGHLIGHTS OF PRESCRIBING INFORMATION

These highlights do not include all the information needed to use CONTRAVE® safely and effectively. See full prescribing information for CONTRAVE.
CONTRAVE (naltrexone hydrochloride and bupropion hydrochloride) extended-release tablets, for oral use
Initial U.S. Approval: 2014

WARNING: SUICIDAL THOUGHTS AND BEHAVIORS

See full prescribing information for complete boxed warning

- Increased risk of suicidal thinking and behavior in children, adolescents, and young adults taking antidepressants for major depressive disorder and other psychiatric disorders. (5.1)
- Monitor for worsening and emergence of suicidal thoughts and behaviors. (5.1)
- CONTRAVE is not approved for use in pediatric patients. (5.1)

1 INDICATIONS AND USAGE

CONTRAVE is a combination of naltrexone, an opioid antagonist, and bupropion, an aminoketone antidepressant, indicated in combination with a reduced-calorie diet and increased physical activity to reduce excess body weight and maintain weight reduction long term in adults with obesity or overweight in the presence of at least one weight-related comorbid condition. (1)

Limitations of Use:

- The effect of CONTRAVE on cardiovascular morbidity and mortality has not been established. (1)
- Coadministration with other naltrexone-containing products is not recommended. Coadministration with other bupropion-containing products is contraindicated. (1, 4)

2 DOSAGE AND ADMINISTRATION

CONTRAVE dose escalation schedule (2.1):

 | Morning Dose | Evening Dose
Week 1 | 1 tablet | None
Week 2 | 1 tablet | 1 tablet
Week 3 | 2 tablets | 1 tablet
Week 4 – Onward | 2 tablets | 2 tablets

3 DOSAGE FORMS AND STRENGTHS

Extended-Release Tablets: 8 mg naltrexone hydrochloride (HCl) /90 mg bupropion HCl (3)

4 CONTRAINDICATIONS

- Uncontrolled hypertension (4)
- Seizure disorders, anorexia nervosa or bulimia, or undergoing abrupt discontinuation of alcohol, benzodiazepines, barbiturates, and antiepileptic drugs (4)
- Use of other bupropion-containing products (4)
- Chronic opioid use (4)
- During or within 14 days of taking monoamine oxidase inhibitors (MAOI) (4)
- Known allergy to any of the ingredients in CONTRAVE (4)

5 WARNINGS AND PRECAUTIONS

- Suicidal Behavior and Ideation: Monitor for depression or suicidal thoughts. Discontinue CONTRAVE if symptoms develop. (5.1)
- Neuropsychiatric Adverse Events During Smoking Cessation: Postmarketing reports of serious or clinically significant neuropsychiatric adverse events have included changes in mood (including depression and mania), psychosis, hallucinations, paranoia, delusions, homicidal ideation, aggression, hostility, agitation, anxiety, and panic, as well as suicidal ideation, suicide attempt, and completed suicide. Observe patients taking CONTRAVE for the occurrence of such symptoms and instruct them to discontinue CONTRAVE and contact a healthcare provider if they experience such adverse events. (5.2)
- Risk of seizure may be minimized by adhering to the recommended dosing schedule and avoiding coadministration with high-fat meal. (5.3)
- Increase in Blood Pressure and Heart Rate: Monitor blood pressure and heart rate in all patients, especially those with cardiac or cerebrovascular disease. (5.5)
- Hepatotoxicity: Cases of hepatitis and clinically significant liver dysfunction observed with naltrexone exposure. (5.7)
- Angle-closure glaucoma: Angle-closure glaucoma has occurred in patients with untreated anatomically narrow angles treated with antidepressants. (5.9)
- Use of Antidiabetic Medications: Weight loss may cause hypoglycemia. Monitor blood glucose. (5.10)

6 ADVERSE REACTIONS

- Most common adverse reactions (greater than or equal to 5%): nausea, constipation, headache, vomiting, dizziness, insomnia, dry mouth and diarrhea. (6.1)

To report SUSPECTED ADVERSE REACTIONS, contact Currax Pharmaceuticals LLC at 1-800-793-2145 or FDA at 1-800-FDA-1088 or www.fda.gov/medwatch.

7 DRUG INTERACTIONS

- MAOIs: Increased risk of hypertensive reactions can occur when used concomitantly. (7.1)
- Drugs Metabolized by CYP2D6: Bupropion inhibits CYP2D6 and can increase concentrations of antidepressants, (e.g., selective serotonin reuptake inhibitors and many tricyclics), antipsychotics (e.g., haloperidol, risperidone and thioridazine), beta-blockers (e.g., metoprolol) and Type 1C antiarrhythmics (e.g., propafenone and flecainide). Consider dose reduction when using with CONTRAVE. (7.3)
- Digoxin: May decrease plasma digoxin levels. Monitor digoxin levels. (7.3)
- Concomitant Treatment with CYP2B6 Inhibitors (e.g., ticlopidine or clopidogrel) can increase bupropion exposure. Do not exceed one tablet twice daily when taken with CYP2B6 inhibitors. (2.5, 7.4)
- CYP2B6 Inducers (e.g., ritonavir, lopinavir, efavirenz, carbamazepine, phenobarbital, and phenytoin) may reduce efficacy by reducing bupropion exposure, avoid concomitant use. (7.4)
- Drugs that Lower Seizure Threshold: Dose CONTRAVE with caution. (5.3, 7.5)
- Dopaminergic Drugs (levodopa and amantadine): CNS toxicity can occur when used concomitantly with CONTRAVE. (7.6)
- Drug-Laboratory Test Interactions: CONTRAVE can cause false- positive urine test results for amphetamines. (7.8)

8 USE IN SPECIFIC POPULATIONS

- Pregnancy: Weight loss during pregnancy may cause fetal harm. Discontinue when a pregnancy is recognized. (8.1)
- Pediatric Use: Safety and effectiveness not established and use not recommended. (8.4)

FULL PRESCRIBING INFORMATION

WARNING: SUICIDAL THOUGHTS AND BEHAVIORS

SUICIDALITY AND ANTIDEPRESSANT DRUGS

CONTRAVE® is not approved for use in the treatment of major depressive disorder or other psychiatric disorders. CONTRAVE contains bupropion, the same active ingredient as some antidepressant medications (including, but not limited to, WELLBUTRIN, WELLBUTRIN SR, WELLBUTRIN XL, and APLENZIN). Antidepressants increased the risk of suicidal thoughts and behavior in children, adolescents, and young adults in short-term trials. These trials did not show an increase in the risk of suicidal thoughts and behavior with antidepressant use in subjects over age 24; there was a reduction in risk with antidepressant use in subjects aged 65 and older. In patients of all ages who are started on CONTRAVE, monitor closely for worsening, and for the emergence of suicidal thoughts and behaviors. Advise families and caregivers of the need for close observation and communication with the prescriber. CONTRAVE is not approved for use in pediatric patients [see Warnings and Precautions (5.1), Use in Specific Populations (8.4)].

1 INDICATIONS AND USAGE

CONTRAVE is indicated in combination with a reduced-calorie diet and increased physical activity to reduce excess body weight and maintain weight reduction long term in adults with obesity or overweight in the presence of at least one weight-related comorbid condition.

Limitations of Use:

- The effect of CONTRAVE on cardiovascular morbidity and mortality has not been established.
- CONTRAVE contains naltrexone and bupropion. Coadministration with other naltrexone-containing products is not recommended. Coadministration with other bupropion-containing products is contraindicated.

2 DOSAGE AND ADMINISTRATION

2.1 Recommended Dosage

Initiate and escalate the dosage of CONTRAVE according to the schedule in Table 1:

Table 1. Dosage Initiation and Escalation Schedule for CONTRAVE
 | Morning Dose | Evening Dose
Week 1 | 1 tablet | None
Week 2 | 1 tablet | 1 tablet
Week 3 | 2 tablets | 1 tablet
Week 4 – Onward | 2 tablets | 2 tablets

A total daily dosage of 32 mg of naltrexone hydrochloride (HCl) and 360 mg bupropion HCl (two CONTRAVE 8 mg/90 mg tablets twice daily) is reached at the start of Week 4.

CONTRAVE should be taken by mouth in the morning and in the evening. The tablets should not be cut, chewed, or crushed. Total daily doses greater than 32 mg/360 mg per day (two tablets twice daily) are not recommended. In clinical trials, CONTRAVE was administered with meals. However, CONTRAVE should not be taken with a high-fat meal because of a resulting significant increase in bupropion and naltrexone systemic exposure [see Warnings and Precautions (5.3) and Clinical Pharmacology (12.3)].

Patients may develop elevated blood pressure or heart rate during CONTRAVE treatment; the risk may be greater during the initial three months of therapy [see Warnings and Precautions (5.6)]. Because patients with hypertension may be at increased risk for developing blood pressure elevations, such patients should be monitored for this potential effect when initiating treatment with CONTRAVE.

Response to therapy should be evaluated after 12 weeks at the maintenance dosage. If a patient has not lost at least 5% of baseline body weight, discontinue CONTRAVE, as it is unlikely that the patient will achieve and sustain clinically meaningful weight loss with continued treatment.

2.2 Dose Adjustment in Patients with Renal Impairment

In patients with moderate or severe renal impairment, the maximum recommended daily dose for CONTRAVE is two tablets (one tablet each morning and evening). CONTRAVE is not recommended for use in patients with end-stage renal disease [see Use in Specific Population (8.6) and Clinical Pharmacology (12.3)].

2.3 Dose Adjustment in Patients with Hepatic Impairment

In patients with moderate hepatic impairment, the maximum recommended daily maintenance dose of CONTRAVE is two tablets (one tablet each morning and evening). CONTRAVE is not recommended for use in patients with severe hepatic impairment [see Use in Specific Population (8.7) and Clinical Pharmacology (12.3)].

2.4 Switching a Patient To or From a Monoamine Oxidase Inhibitor (MAOI) Antidepressant

At least 14 days should elapse between discontinuation of an MAOI intended to treat depression and initiation of therapy with CONTRAVE. Conversely, at least 14 days should be allowed after stopping CONTRAVE before starting an MAOI antidepressant [see Contraindications (4) and Drug Interactions (7.1)].

2.5 Concomitant Use with CYP2B6 Inhibitors

During concomitant use with CYP2B6 inhibitors (e.g., ticlopidine or clopidogrel), the maximum recommended daily dose of CONTRAVE is two tablets (one tablet each morning and evening) [see Drug Interactions (7.4) and Clinical Pharmacology (12.3)].

3 DOSAGE FORMS AND STRENGTHS

CONTRAVE extended-release tablets: 8 mg/90 mg are blue, round, bi-convex, film-coated, and debossed with "NB-890" on one side.

4 CONTRAINDICATIONS

CONTRAVE is contraindicated in

- Uncontrolled hypertension [see Warnings and Precautions (5.5)]
- Seizure disorder or a history of seizures [see Warnings and Precautions (5.3)]
- Use of other bupropion-containing products (including, but not limited to, WELLBUTRIN, WELLBUTRIN SR, WELLBUTRIN XL, APLENZIN and ZYBAN)
- Bulimia or anorexia nervosa, which increase the risk for seizure [see Warnings and Precautions (5.3)]
- Chronic opioid or opiate agonist (e.g., methadone) or partial agonists (e.g., buprenorphine) use, or acute opiate withdrawal [see Warnings and Precautions (5.4) and Drug Interactions (7.2)]
- Patients undergoing an abrupt discontinuation of alcohol, benzodiazepines, barbiturates, and antiepileptic drugs [see Warnings and Precautions (5.3) and Drug Interactions (7.7)]
- Concomitant administration of monoamine oxidase inhibitors (MAOI). At least 14 days should elapse between discontinuation of MAOI and initiation of treatment with CONTRAVE. There is an increased risk of hypertensive reactions when CONTRAVE is used concomitantly with MAOIs. Starting CONTRAVE in a patient treated with reversible MAOIs such as linezolid or intravenous methylene blue is also contraindicated [see Dosage and Administration (2.4), Drug Interactions (7.1)]
- Known allergy to bupropion, naltrexone or any other component of CONTRAVE. Anaphylactoid/anaphylactic reactions and Stevens-Johnson syndrome have been reported with bupropion [see Warnings and Precautions (5.6)]

5 WARNINGS AND PRECAUTIONS

5.1 Suicidal Behavior and Ideation

CONTRAVE contains bupropion, a dopamine and norepinephrine re-uptake inhibitor that is similar to some drugs used for the treatment of depression; therefore, the following precautions pertaining to these products should be considered when treating patients with CONTRAVE.

Patients with major depressive disorder, both adult and pediatric, may experience worsening of their depression and/or the emergence of suicidal ideation and behavior (suicidality) or unusual changes in behavior, whether or not they are taking antidepressant medications, and this risk may persist until significant remission occurs. Suicide is a known risk of depression and certain other psychiatric disorders, and these disorders themselves are the strongest predictors of suicide. There has been a long-standing concern that antidepressants may have a role in inducing worsening of depression and the emergence of suicidality in certain patients during the early phases of treatment.

In placebo-controlled clinical trials with CONTRAVE for the treatment of obesity in adult patients, no suicides or suicide attempts were reported in studies up to 56 weeks duration with CONTRAVE (equivalent to bupropion doses of 360 mg/day). In these same studies, suicidal ideation was reported by 3 (0.20%) of 1,515 patients treated with placebo compared with 1 (0.03%) of 3,239 treated with CONTRAVE.

Pooled analyses of short-term placebo-controlled trials of antidepressant drugs (selective serotonin re-uptake inhibitors [SSRIs] and others) show that these drugs increase the risk of suicidal thinking and behavior (suicidality) in children, adolescents, and young adults (ages 18 to 24) with major depressive disorder (MDD) and other psychiatric disorders. Short-term clinical trials did not show an increase in the risk of suicidality with antidepressants compared with placebo in adults beyond age 24; there was a reduction with antidepressants compared with placebo in adults aged 65 and older. CONTRAVE is not approved for use in pediatric patients.

The pooled analyses of placebo-controlled trials of antidepressant drugs in children and adolescents with MDD, obsessive compulsive disorder (OCD), or other psychiatric disorders included a total of 24 short-term trials of nine antidepressant drugs in over 4,400 patients. The pooled analyses of placebo-controlled trials in adults with MDD or other psychiatric disorders included a total of 295 short-term trials (median duration of two months) of 11 antidepressant drugs in over 77,000 patients. There was considerable variation in risk of suicidality among drugs, but a tendency toward an increase in the younger patients for almost all drugs studied. There were differences in absolute risk of suicidality across the different indications, with the highest incidence in MDD. The risk differences (drug vs placebo), however, were relatively stable within age strata and across indications. These risk differences (drug-placebo difference in the number of cases of suicidality per 1,000 patients treated) are provided in Table 2.

Table 2. Risk Differences in the Number of Suicidality Cases by Age Group in the Pooled Placebo-Controlled Trials of Antidepressants in Pediatric and Adult Subjects
Age Range | Drug-Placebo Difference in Number of Cases of Suicidality per 1,000 Patients Treated
 | Increases Compared to Placebo
<18 | 14 additional cases
18 to 24 | 5 additional cases
 | Decreases Compared to Placebo
25 to 64 | 1 fewer case
≥65 | 6 fewer cases

No suicides occurred in any of the antidepressant pediatric trials. There were suicides in the adult antidepressant trials, but the number was not sufficient to reach any conclusion about drug effect on suicide.

It is unknown whether the suicidality risk extends to longer-term use, i.e., beyond several months. However, there is substantial evidence from placebo-controlled trials in adults with depression that the use of antidepressants can delay the recurrence of depression.

All patients being treated with antidepressants for any indication should be monitored appropriately and observed closely for clinical worsening, suicidality, and unusual changes in behavior, especially during the initial few months of a course of drug therapy, or at times of dose changes, either increases or decreases. This warning applies to CONTRAVE because one of its components, bupropion, is a member of an antidepressant class.

The following symptoms, anxiety, agitation, panic attacks, insomnia, irritability, hostility, aggressiveness, impulsivity, akathisia (psychomotor restlessness), hypomania, and mania, have been reported in adult and pediatric patients being treated with antidepressants for major depressive disorder as well as for other indications, both psychiatric and nonpsychiatric. Although a causal link between the emergence of such symptoms and either the worsening of depression and/or the emergence of suicidal impulses has not been established, there is concern that such symptoms may represent precursors to emerging suicidality.

Consideration should be given to changing the therapeutic regimen, including possibly discontinuing the medication, in patients whose depression is persistently worse, or who are experiencing emergent suicidality or symptoms that might be precursors to worsening depression or suicidality, especially if these symptoms are severe, abrupt in onset, or were not part of the patient's presenting symptoms.

Families and caregivers of patients being treated with antidepressants for major depressive disorder or other indications, both psychiatric and nonpsychiatric, should be alerted about the need to monitor patients for the emergence of anxiety, agitation, irritability, unusual changes in behavior, and the other symptoms described above, as well as the emergence of suicidality, and to report such symptoms immediately to healthcare providers. Such monitoring should include daily observation by families and caregivers. Prescriptions for CONTRAVE should be written for the smallest quantity of tablets consistent with good patient management, in order to reduce the risk of overdose.

5.2 Neuropsychiatric Adverse Events and Suicide Risk in Smoking Cessation Treatment

CONTRAVE is not approved for smoking cessation treatment, but serious neuropsychiatric adverse events have been reported in patients taking bupropion for smoking cessation. These postmarketing reports have included changes in mood (including depression and mania), psychosis, hallucinations, paranoia, delusions, homicidal ideation, aggression, hostility, agitation, anxiety, and panic, as well as suicidal ideation, suicide attempt, and completed suicide [see Warnings and Precautions (5.1)]. Some patients who stopped smoking may have been experiencing symptoms of nicotine withdrawal, including depressed mood. Depression, rarely including suicidal ideation, has been reported in smokers undergoing a smoking cessation attempt without medication. However, some of these adverse events occurred in patients taking bupropion who continued to smoke.

Neuropsychiatric adverse events occurred in patients without and with pre-existing psychiatric disease; some patients experienced worsening of their psychiatric illnesses. Observe patients for the occurrence of neuropsychiatric adverse events. Advise patients and caregivers that the patient should stop taking CONTRAVE and contact a healthcare provider immediately if agitation, depressed mood, or changes in behavior or thinking that are not typical for the patient are observed, or if the patient develops suicidal ideation or suicidal behavior. In many postmarketing cases, resolution of symptoms after discontinuation of bupropion was reported. However, the symptoms persisted in some cases, therefore, ongoing monitoring and supportive care should be provided until symptoms resolve.

Depression, suicide, attempted suicide and suicidal ideation have been reported in the postmarketing experience with naltrexone used in the treatment of opioid dependence. No causal relationship has been demonstrated.

5.3 Seizures

Bupropion, a component of CONTRAVE, can cause seizures. The risk of seizure is dose- related. The incidence of seizure in patients receiving CONTRAVE in clinical trials was approximately 0.1% vs 0% on placebo. CONTRAVE should be discontinued and not restarted in patients who experience a seizure while being treated with CONTRAVE.

The risk of seizures is also related to patient factors, clinical situations, and concomitant medications that lower the seizure threshold. Consider these risks before initiating treatment with CONTRAVE. CONTRAVE is contraindicated in patients with a seizure disorder, current or prior diagnosis of anorexia nervosa or bulimia, or undergoing abrupt discontinuation of alcohol, benzodiazepines, barbiturates, and antiepileptic drugs. Caution should be used when prescribing CONTRAVE to patients with predisposing factors that may increase the risk of seizure including:

- history of head trauma or prior seizure, severe stroke, arteriovenous malformation, central nervous system tumor or infection, or metabolic disorders (e.g., hypoglycemia, hyponatremia, severe hepatic impairment, and hypoxia)
- excessive use of alcohol or sedatives, addiction to cocaine or stimulants, or withdrawal from sedatives
- patients with diabetes treated with insulin and/or oral diabetic medications (sulfonylureas and meglitinides) that may cause hypoglycemia
- concomitant administration of medications that may lower the seizure threshold, including other bupropion products, antipsychotics, tricyclic antidepressants, theophylline, systemic steroids

Recommendations for Reducing the Risk of Seizure: Clinical experience with bupropion suggests that the risk of seizure may be minimized by adhering to the recommended dosing recommendations [see Dosage and Administration (2)], in particular:

- the total daily dose of CONTRAVE does not exceed 360 mg of the bupropion component (i.e., four tablets per day)
- the daily dose is administered in divided doses (twice daily)
- the dose is escalated gradually
- no more than two tablets are taken at one time
- coadministration of CONTRAVE with high-fat meals is avoided [see Dosage and Administration (2.1) and Clinical Pharmacology (12.3)]
- if a dose is missed, a patient should wait until the next scheduled dose to resume the regular dosing schedule

5.4 Patients Receiving Opioid Analgesics

Vulnerability to Opioid Overdose: CONTRAVE should not be administered to patients receiving chronic opioids, due to the naltrexone component, which is an opioid receptor antagonist [see Contraindications (4)]. If chronic opiate therapy is required, CONTRAVE treatment should be stopped. In patients requiring intermittent opiate treatment, CONTRAVE therapy should be temporarily discontinued and lower doses of opioids may be needed. Patients should be alerted that they may be more sensitive to opioids, even at lower doses, after CONTRAVE treatment is discontinued.

An attempt by a patient to overcome any naltrexone opioid blockade by administering large amounts of exogenous opioids is especially dangerous and may lead to a fatal overdose or life-threatening opioid intoxication (e.g., respiratory arrest, circulatory collapse). Patients should be told of the serious consequences of trying to overcome the opioid blockade.

Precipitated Opioid Withdrawal: The symptoms of spontaneous opioid withdrawal, which are associated with the discontinuation of opioid in a dependent individual, are uncomfortable, but they are not generally believed to be severe or necessitate hospitalization. However, when withdrawal is precipitated abruptly, the resulting withdrawal syndrome can be severe enough to require hospitalization. To prevent occurrence of either precipitated withdrawal in patients dependent on opioids or exacerbation of a pre-existing subclinical withdrawal symptoms, opioid-dependent patients, including those being treated for alcohol dependence, should be opioid-free (including tramadol) before starting CONTRAVE treatment. An opioid-free interval of a minimum of 7 to 10 days is recommended for patients previously dependent on short- acting opioids, and those patients transitioning from buprenorphine or methadone may need as long as two weeks. Patients should be made aware of the risks associated with precipitated withdrawal and encouraged to give an accurate account of last opioid use.

5.5 Increase in Blood Pressure and Heart Rate

CONTRAVE can cause an increase in systolic and/or diastolic blood pressure as well as an increase in resting heart rate. In clinical practice with other bupropion-containing products, hypertension, in some cases severe and requiring acute treatment, has been reported. The clinical significance of the increases in blood pressure and heart rate observed with CONTRAVE treatment is unclear, especially for patients with cardiac and cerebrovascular disease, since patients with a history of myocardial infarction or stroke in the previous 6 months, life-threatening arrhythmias, or congestive heart failure were excluded from CONTRAVE clinical trials. Blood pressure and pulse should be measured prior to starting therapy with CONTRAVE and should be monitored at regular intervals consistent with usual clinical practice, particularly among patients with controlled hypertension prior to treatment [see Dosage and Administration (2.1)]. CONTRAVE should not be given to patients with uncontrolled hypertension [see Contraindications (4)].

Among patients treated with CONTRAVE in placebo-controlled clinical trials, mean systolic and diastolic blood pressure was approximately 1 mmHg higher than baseline at Weeks 4 and 8, similar to baseline at Week 12, and approximately 1 mmHg below baseline between Weeks 24 and 56. In contrast, among patients treated with placebo, mean blood pressure was approximately 2 to 3 mmHg below baseline throughout the same time points, yielding statistically significant differences between the groups at every assessment during this period. The largest mean differences between the groups were observed during the first 12 weeks (treatment difference +1.8 to +2.4 mmHg systolic, all p<0.001; +1.7 to +2.1 mmHg diastolic, all p<0.001).

For heart rate, at both Weeks 4 and 8, mean heart rate was statistically significantly higher (2.1 bpm) in the CONTRAVE group compared with the placebo group; at Week 52, the difference between groups was +1.7 bpm (p<0.001).

In an ambulatory blood pressure monitoring substudy of 182 patients, the mean change from baseline in systolic blood pressure after 52 weeks of treatment was -0.2 mmHg for the CONTRAVE group and -2.8 mmHg for the placebo group (treatment difference, +2.6 mmHg, p=0.08); the mean change in diastolic blood pressure was +0.8 mmHg for the CONTRAVE group and -2.1 mmHg for the placebo group (treatment difference, +2.9 mmHg, p=0.004).

A greater percentage of subjects had adverse reactions related to blood pressure or heart rate in the CONTRAVE group compared to the placebo group (6.3% vs 4.2%, respectively), primarily attributable to adverse reactions of Hypertension/Blood Pressure Increased (5.9% vs 4.0%, respectively). These events were observed in both patients with and without evidence of preexisting hypertension. In a trial that enrolled individuals with diabetes, 12.0% of patients in the CONTRAVE group and 6.5% in the placebo group had a blood pressure-related adverse reaction.

5.6 Allergic Reactions

Anaphylactoid/anaphylactic reactions characterized by symptoms such as pruritus, urticaria, angioedema, and dyspnea requiring medical treatment have been reported in clinical trials with bupropion. In addition, there have been rare spontaneous postmarketing reports of erythema multiforme, Stevens-Johnson syndrome, and anaphylactic shock associated with bupropion. Instruct patients to discontinue CONTRAVE and consult a healthcare provider if they develop an allergic or anaphylactoid/anaphylactic reaction (e.g., skin rash, pruritus, hives, chest pain, edema, or shortness of breath) during treatment.

Arthralgia, myalgia, fever with rash, and other symptoms suggestive of delayed hypersensitivity have been reported in association with bupropion. These symptoms may resemble serum sickness.

5.7 Hepatotoxicity

Cases of hepatitis and clinically significant liver dysfunction were observed in association with naltrexone exposure during naltrexone clinical trials and in postmarketing reports for patients using naltrexone. Transient, asymptomatic hepatic transaminase elevations were also observed. When patients presented with elevated transaminases, there were often other potential causative or contributory etiologies identified, including pre-existing alcoholic liver disease, hepatitis B and/or C infection, and concomitant usage of other potentially hepatotoxic drugs. Although clinically significant liver dysfunction is not typically recognized as a manifestation of opioid withdrawal, opioid withdrawal that is precipitated abruptly may lead to systemic sequelae, including acute liver injury.

Patients should be warned of the risk of hepatic injury and advised to seek medical attention if they experience symptoms of acute hepatitis. Use of CONTRAVE should be discontinued in the event of symptoms and/or signs of acute hepatitis.

In CONTRAVE clinical trials, there were no cases of elevated transaminases greater than three times the upper limit of normal (ULN) in conjunction with an increase in bilirubin greater than two times ULN.

5.8 Activation of Mania

Bupropion, a component of CONTRAVE, is a drug used for the treatment of depression. Antidepressant treatment can precipitate a manic, mixed, or hypomanic episode. The risk appears to be increased in patients with bipolar disorder or who have risk factors for bipolar disorder. Prior to initiating CONTRAVE, screen patients for a history of bipolar disorder and the presence of risk factors for bipolar disorder (e.g., family history of bipolar disorder, suicide, or depression). CONTRAVE is not approved for use in treating bipolar depression. No activation of mania or hypomania was reported in the clinical trials evaluating effects of CONTRAVE in obese patients; however, patients receiving antidepressant medications and patients with a history of bipolar disorder or recent hospitalization because of psychiatric illness were excluded from CONTRAVE clinical trials.

5.9 Angle-Closure Glaucoma

The pupillary dilation that occurs following use of many antidepressant drugs including bupropion, a component of CONTRAVE, may trigger an angle-closure attack in a patient with anatomically narrow angles who does not have a patent iridectomy.

5.10 Potential Risk of Hypoglycemia in Patients with Type 2 Diabetes Mellitus on Antidiabetic Therapy

Weight loss may increase the risk of hypoglycemia in patients with type 2 diabetes mellitus treated with insulin and/or insulin secretagogues (e.g., sulfonylureas). Measurement of blood glucose levels prior to starting CONTRAVE and during CONTRAVE treatment is recommended in patients with type 2 diabetes. Decreases in medication doses for antidiabetic medications which are non-glucose-dependent should be considered to mitigate the risk of hypoglycemia. If a patient develops hypoglycemia after starting CONTRAVE, appropriate changes should be made to the antidiabetic drug regimen.

6 ADVERSE REACTIONS

The following adverse reactions are discussed in other sections of the labeling:

- Suicidal Behavior and Ideation [see Boxed Warning, Warnings and Precautions (5.1)]
- Neuropsychiatric Adverse Events [see Warnings and Precautions (5.2)]
- Seizures [see Contraindications (4), Warnings and Precautions (5.3)]
- Increase in Blood Pressure and Heart Rate [see Warnings and Precautions (5.5)]
- Allergic Reactions [see Warnings and Precautions (5.6)]
- Angle-Closure Glaucoma [see Warnings and Precautions (5.9)]

6.1 Clinical Trials Experience

Because clinical trials are conducted under widely varying conditions, the adverse reaction rates observed in the clinical trials of a drug cannot be directly compared to rates in the clinical trials of another drug and may not reflect the rates observed in practice.

CONTRAVE was evaluated for safety in five double-blind placebo-controlled trials in 4,754 overweight or obese patients (3,239 patients treated with CONTRAVE and 1,515 patients treated with placebo) for a treatment period up to 56 weeks. The majority of patients were treated with CONTRAVE 32 mg/360 mg total daily dose. In addition, some patients were treated with other combination daily doses including naltrexone up to 50 mg and bupropion up to 400 mg. All subjects received study drug in addition to diet and exercise counseling. One trial (N=793) evaluated patients participating in an intensive behavioral modification program and another trial (N= 505) evaluated patients with type 2 diabetes. In these randomized, placebo-controlled trials, 2,545 patients received CONTRAVE 32 mg/360 mg for a mean treatment duration of 36 weeks (median, 56 weeks). Baseline patient characteristics included a mean age of 46 years, 82% women, 78% white, 25% with hypertension, 13% with type 2 diabetes, 56% with dyslipidemia, 25% with BMI greater than 40 kg/m^2, and less than 2% with coronary artery disease. Dosing was initiated and increased weekly to reach the maintenance dose within 4 weeks.

In CONTRAVE clinical trials, 24% of subjects receiving CONTRAVE and 12% of subjects receiving placebo discontinued treatment because of an adverse event. The most frequent adverse reactions leading to discontinuation with CONTRAVE were nausea (6.3%), headache (1.7%) and vomiting (1.1%).

Common Adverse Reactions

Adverse reactions that were reported by greater than or equal to 2% of patients and were more frequently reported by patients treated with CONTRAVE compared to placebo, are summarized in Table 3.

Table 3. Adverse Reactions Reported by Obese or Overweight Patients With an Incidence (%) of at Least 2% Among Patients Treated with CONTRAVE and More Common than with Placebo
Adverse Reaction | CONTRAVE 32 mg/360 mg N=2545 % | Placebo N=1515 %
Nausea | 32.5 | 6.7
Constipation | 19.2 | 7.2
Headache | 17.6 | 10.4
Vomiting | 10.7 | 2.9
Dizziness | 9.9 | 3.4
Insomnia | 9.2 | 5.9
Dry mouth | 8.1 | 2.3
Diarrhea | 7.1 | 5.2
Anxiety | 4.2 | 2.8
Hot flush | 4.2 | 1.2
Fatigue | 4.0 | 3.4
Tremor | 4.0 | 0.7
Upper abdominal pain | 3.5 | 1.3
Viral gastroenteritis | 3.5 | 2.6
Influenza | 3.4 | 3.2
Tinnitus | 3.3 | 0.6
Urinary tract infection | 3.3 | 2.8
Hypertension | 3.2 | 2.2
Abdominal pain | 2.8 | 1.4
Hyperhidrosis | 2.6 | 0.6
Irritability | 2.6 | 1.8
Blood pressure increased | 2.4 | 1.5
Dysgeusia | 2.4 | 0.7
Rash | 2.4 | 2.0
Muscle strain | 2.2 | 1.7
Palpitations | 2.1 | 0.9

Other Adverse Reactions

The following additional adverse reactions were reported in less than 2% of patients treated with CONTRAVE but with an incidence at least twice that of placebo:

Cardiac Disorders: tachycardia, myocardial infarction
Ear and Labyrinth Disorders: vertigo, motion sickness
Gastrointestinal Disorders: lower abdominal pain, eructation, lip swelling, hematochezia, hernia
General Disorders and Administration Site Conditions: feeling jittery, feeling abnormal, asthenia, thirst, feeling hot
Hepatobiliary Disorders: cholecystitis
Infections and Infestations: pneumonia, staphylococcal infection, kidney infection
Investigations: increased blood creatinine, increased hepatic enzymes, decreased hematocrit
Metabolism and Nutrition Disorders: dehydration
Musculoskeletal and Connective Tissue Disorders: intervertebral disc protrusion, jaw pain
Nervous System Disorders: disturbance in attention, lethargy, intention tremor, balance
disorder, memory impairment, amnesia, mental impairment, presyncope
Psychiatric Disorders: abnormal dreams, nervousness, dissociation (feeling spacey), tension, agitation, mood swings
Renal and Urinary Disorders: micturition urgency
Reproductive System and Breast Disorders: vaginal hemorrhage, irregular menstruation, erectile dysfunction, vulvovaginal dryness
Skin and Subcutaneous Tissue Disorders: alopecia

Psychiatric and Sleep Disorders

In the one-year controlled trials of CONTRAVE, the proportion of patients reporting one or more adverse reactions related to psychiatric and sleep disorders was higher in the CONTRAVE 32/360 mg group than the placebo group (22.2% and 15.5%, respectively). These events were further categorized into sleep disorders (13.8% CONTRAVE, 8.4% placebo), depression (6.3% CONTRAVE, 5.9% placebo), and anxiety (6.1% CONTRAVE, 4.4% placebo). Patients who were 65 years or older experienced more psychiatric and sleep disorder adverse reactions in the CONTRAVE group (28.6%) compared to placebo (6.3%), although the sample size in this subgroup was small (56 CONTRAVE, 32 placebo); the majority of these events were insomnia (10.7% CONTRAVE, 3.1% placebo) and depression (7.1% CONTRAVE, 3.1% placebo).

Neurocognitive Adverse Reactions

Adverse reactions involving attention, dizziness, and syncope occurred more often in individuals randomized to CONTRAVE 32/360 mg group compared to placebo (15.0% and 5.5%, respectively). The most common cognitive-related adverse reactions were attention disorders (2.5% CONTRAVE, 0.6% placebo). Adverse reactions involving dizziness and syncope were more common in patients treated with CONTRAVE (10.6%) than in placebo-treated patients (3.6%); dizziness accounted for almost all of these reported events (10.4% CONTRAVE, 3.4% placebo). Dizziness was the primary reason for discontinuation for 0.9% and 0.3% of patients in the CONTRAVE and placebo groups, respectively.

Increases in Serum Creatinine

In the one-year controlled trials of CONTRAVE, larger mean increases in serum creatinine from baseline to trial endpoint were observed in the CONTRAVE group compared with the placebo group (0.07 mg/dL and 0.01 mg/dL, respectively) as well as from baseline to the maximum value during follow-up (0.15 mg/dL and 0.07 mg/dL, respectively). Increases in serum creatinine that exceeded the upper limit of normal and were also greater than or equal to 50% higher than baseline occurred in 0.6% of subjects receiving CONTRAVE compared to 0.1% receiving placebo. The observed increase in serum creatinine may be the result of OCT2 inhibition [see Clinical Pharmacology (12.3)].

6.2 Postmarketing Experience

The following adverse reactions have been identified during post approval use of CONTRAVE, naltrexone, or bupropion. Because these reactions are reported voluntarily from a population of uncertain size, it is not always possible to reliably estimate their frequency or establish a causal relationship to drug exposure.

- Loss of consciousness, malaise
- Brugada pattern/syndrome
- Drug reaction with eosinophilia and systemic symptoms (DRESS)
- Acute generalized exanthematous pustulosis (AGEP)
- Aseptic meningitis

7 DRUG INTERACTIONS

7.1 Monoamine Oxidase Inhibitors (MAOI)

Concomitant use of MAOIs and bupropion is contraindicated. Bupropion inhibits the re-uptake of dopamine and norepinephrine and can increase the risk for hypertensive reactions when used concomitantly with drugs that also inhibit the re-uptake of dopamine or norepinephrine, including MAOIs. Studies in animals demonstrate that the acute toxicity of bupropion is enhanced by the MAOI phenelzine. At least 14 days should elapse between discontinuation of an MAOI and initiation of treatment with CONTRAVE. Conversely, at least 14 days should be allowed after stopping CONTRAVE before starting an MAOI [see Contraindications (4)].

7.2 Opioid Analgesics

Patients taking CONTRAVE may not fully benefit from treatment with opioid-containing medicines, such as cough and cold remedies, antidiarrheal preparations, and opioid analgesics. In patients requiring intermittent opiate treatment, CONTRAVE therapy should be temporarily discontinued, and opiate dose should not be increased above the standard dose. CONTRAVE may be used with caution after chronic opioid use has been stopped for 7 to 10 days in order to prevent precipitation of withdrawal [see Contraindications (4) and Warnings and Precautions (5.4)].

During CONTRAVE clinical studies, the use of concomitant opioid or opioid-like medications, including analgesics or antitussives, were excluded.

7.3 Potential for CONTRAVE to Affect Other Drugs

Metabolized by CYP2D6

In a clinical study, CONTRAVE (32 mg naltrexone/360 mg bupropion) daily was coadministered with a 50 mg dose of metoprolol (a CYP2D6 substrate). CONTRAVE increased metoprolol AUC and Cmax by approximately 4- and 2-fold, respectively, relative to metoprolol alone. Similar clinical drug interactions resulting in increased pharmacokinetic exposure of CYP2D6 substrates have also been observed with bupropion as a single agent with desipramine or venlafaxine.

Coadministration of CONTRAVE with drugs that are metabolized by CYP2D6 isozyme including certain antidepressants (SSRIs and many tricyclics), antipsychotics (e.g., haloperidol, risperidone and thioridazine), beta-blockers (e.g., metoprolol) and Type 1C antiarrhythmics (e.g., propafenone and flecainide), should be approached with caution and should be initiated at the lower end of the dose range of the concomitant medication. If CONTRAVE is added to the treatment regimen of a patient already receiving a drug metabolized by CYP2D6, the need to decrease the dose of the original medication should be considered, particularly for those concomitant medications with a narrow therapeutic index [see Clinical Pharmacology (12.3)].

Digoxin

Coadministration of CONTRAVE with digoxin may decrease plasma digoxin levels. Monitor plasma digoxin levels in patients treated concomitantly with CONTRAVE and digoxin [see Clinical Pharmacology (12.3)].

7.4 Potential for Other Drugs to Affect CONTRAVE

Bupropion is primarily metabolized to hydroxybupropion by CYP2B6. Therefore, the potential exists for drug interactions between CONTRAVE and drugs that are inhibitors or inducers of CYP2B6.

Inhibitors of CYP2B6: Ticlopidine and Clopidogrel: Concomitant treatment with these drugs can increase bupropion exposure but decrease hydroxybupropion exposure. During concomitant use with CYP2B6 inhibitors (e.g., ticlopidine or clopidogrel), the CONTRAVE daily dose should not exceed two tablets (one tablet each morning and evening) [see Dosage and Administration (2.5) and Clinical Pharmacology (12.3)].

Inducers of CYP2B6: Ritonavir, Lopinavir, and Efavirenz: Concomitant treatment with these drugs can decrease bupropion and hydroxybupropion exposure and may reduce efficacy. Avoiding concomitant use with ritonavir, lopinavir, or efavirenz is recommended [see Clinical Pharmacology (12.3)].

7.5 Drugs That Lower Seizure Threshold

Use extreme caution when coadministering CONTRAVE with other drugs that lower seizure threshold (e.g., antipsychotics, antidepressants, theophylline, or systemic corticosteroids). Use low initial doses and increase the dose gradually. Concomitant use of other bupropion-containing products is contraindicated [see Contraindications (4) and Warnings and Precautions (5.3)].

7.6 Dopaminergic Drugs (Levodopa and Amantadine)

Bupropion, levodopa, and amantadine have dopamine agonist effects. CNS toxicity has been reported when bupropion was coadministered with levodopa or amantadine. Adverse reactions have included restlessness, agitation, tremor, ataxia, gait disturbance, vertigo, and dizziness. It is presumed that the toxicity results from cumulative dopamine agonist effects. Use caution and monitor for such adverse reactions when administering CONTRAVE concomitantly with these drugs.

7.7 Use with Alcohol

In postmarketing experience, there have been rare reports of adverse neuropsychiatric events or reduced alcohol tolerance in patients who were drinking alcohol during treatment with bupropion. The consumption of alcohol during treatment with CONTRAVE should be minimized or avoided.

7.8 Drug-Laboratory Test Interactions

False-positive urine immunoassay screening tests for amphetamines have been reported in patients taking bupropion. This is due to lack of specificity of some screening tests. False-positive test results may result even following discontinuation of bupropion therapy. Confirmatory tests, such as gas chromatography/mass spectrometry, will distinguish bupropion from amphetamines.

8 USE IN SPECIFIC POPULATIONS

8.1 Pregnancy

Risk Summary

Weight loss offers no benefit to a pregnant patient and may cause fetal harm. When a pregnancy is recognized, advise the pregnant patient of the risk to the fetus, and discontinue CONTRAVE (see Clinical Considerations). Available pharmacovigilance data and data from clinical trials with the individual components of CONTRAVE use in pregnant patients have not demonstrated a drug-associated risk of major birth defects, miscarriage or adverse maternal or fetal outcomes.

Bupropion

Data from epidemiological studies of pregnant patients exposed to bupropion in the first trimester have not identified an increased risk of congenital malformations overall (see Data). When bupropion was administered to pregnant rats during organogenesis, there was no evidence of fetal malformations at doses up to approximately 20 times the maximum recommended human dose (MRHD) of 360 mg/day. When given to pregnant rabbits during organogenesis, non-dose–related increases in incidence of fetal malformations, and skeletal variations were observed at doses approximately twice the MRHD and greater. Decreased fetal weights were seen at doses 5 times the MRHD and greater (see Data).

Naltrexone

Limited case report data of pregnant patients exposed to naltrexone in the first trimester have not identified an increased risk of congenital malformations overall. Daily oral administration of naltrexone during the period of organogenesis has been shown to increase the incidence of early fetal loss in rats and rabbits at doses ≥ 15 times and ≥ 60 times the MRHD of 32 mg/day, respectively. There was no evidence of fetal malformations in rats and rabbits at doses up to approximately 100 and 200 times the MHRD, respectively. (see Data).

The estimated background risk of major birth defects and miscarriage for the indicated population is unknown. In the U.S. general population, the estimated background risk of major birth defects and miscarriage in clinically recognized pregnancies is 2-4% and 15-20%, respectively.

Clinical Considerations

Disease-associated maternal and/or embryo/fetal risk

Appropriate weight gain based on pre-pregnancy weight is currently recommended for all pregnant patients, including those who are already overweight or obese, due to the obligatory weight gain that occurs in maternal tissues during pregnancy.

Data

Human Data

In clinical studies, 21 (0.7%) of 3,024 women became pregnant while taking CONTRAVE: 11 carried to term and gave birth to a healthy infant, three had elective abortions, four had spontaneous abortions, and the outcome of three pregnancies were unknown.

Data from the international bupropion Pregnancy Registry (675 first trimester exposures) and a retrospective cohort study using the United Healthcare database (1,213 first trimester exposures) did not show an increased risk for malformations overall.

No increased risk for cardiovascular malformations overall has been observed after bupropion exposure during the first trimester. The prospectively observed rate of cardiovascular malformations in pregnancies with exposure to bupropion in the first trimester from the international Pregnancy Registry was 1.3% (9 cardiovascular malformations out of 675 first-trimester maternal bupropion exposures), which is similar to the background rate of cardiovascular malformations (approximately 1%). Data from the United Healthcare database and a case-control study (6,853 infants with cardiovascular malformations and 5,763 with non-cardiovascular malformations) from the National Birth Defects Prevention Study (NBDPS) did not show an increased risk for cardiovascular malformations overall after bupropion exposure during the first trimester.

Study findings on bupropion exposure during the first trimester and risk for left ventricular outflow tract obstruction (LVOTO) are inconsistent and do not allow conclusions regarding a possible association. The United Healthcare database lacked sufficient power to evaluate this association; the NBDPS found increased risk for LVOTO (n = 10; adjusted odds ratio [OR] = 2.6; 95% CI: 1.2, 5.7), and the Slone Epidemiology case control study did not find increased risk for LVOTO.

Study findings on bupropion exposure during the first trimester and risk for ventricular septal defect (VSD) are inconsistent and do not allow conclusions regarding a possible association. The Slone Epidemiology Study found an increased risk for VSD following first trimester maternal bupropion exposure (n = 17; adjusted OR = 2.5; 95% CI: 1.3, 5.0) but did not find increased risk for any other cardiovascular malformations studied (including LVOTO as above). The NBDPS and United Healthcare database study did not find an association between first trimester maternal bupropion exposure and VSD.

For the findings of LVOTO and VSD, the studies were limited by the small number of exposed cases, inconsistent findings among studies, and the potential for chance findings from multiple comparisons in case control studies.

Animal Data

Reproduction and developmental studies have not been conducted for the combined products naltrexone and bupropion in CONTRAVE. Separate studies with bupropion and naltrexone have been conducted in pregnant rats and rabbits. Safety margins were estimated using body surface area exposure (mg/m^2) based on a body weight of 100 kg.

Daily oral administration of naltrexone has been shown to increase the incidence of early fetal loss when given to rats at doses ≥30 mg/kg/day (15 times the MHRD on a mg/m^2 basis) and to rabbits at oral doses ≥60 mg/kg/day (60 times the MHRD on a mg/m^2 basis).

Daily oral administration of naltrexone to rats and rabbits during the period of organogenesis did not induce malformations at doses up to 200 mg/kg/day (approximately 100 and 200 times the MHRD, respectively, on a mg/m^2 basis).

Rats do not form appreciable quantities of the major human metabolite, 6-beta-naltrexol; therefore, the potential reproductive toxicity of the metabolite in rats is not known. In studies conducted in pregnant rats and rabbits, bupropion was administered orally during the period of organogenesis at doses of up to 450 and 150 mg/kg/day, respectively (approximately 20 and 14 times the MRHD, respectively, on a mg/m^2 basis). There was no evidence of fetal malformations in rats. When given to pregnant rabbits during organogenesis, non-dose-related increases in incidence of fetal malformations and skeletal variations were observed at the lowest dose tested (25 mg/kg/day, approximately 2 times the MRHD on a mg/m^2 basis) and greater. Decreased fetal weights were observed at doses of 50 mg/kg/day (approximately 5 times the MRHD on a mg/m^2 basis) and greater. No maternal toxicity was evident at doses of 50 mg/kg/day or less.

In a pre- and postnatal development study, bupropion administered orally to pregnant rats at doses of up to 150 mg/kg/day (approximately 7 times the MRHD on a mg/m^2 basis) from embryonic implantation through lactation had no effect on pup growth or development.

8.2 Lactation

Risk Summary

Data from published literature report the presence of bupropion and its metabolites in human milk. Limited data from postmarketing reports with bupropion use during lactation have not identified a clear association of adverse effects on a breastfed infant (see Data). Naltrexone and its major metabolite, 6β-naltrexol, are present in human milk. There are no data on bupropion, naltrexone, or their metabolites on milk production. The developmental and health benefits of breastfeeding should be considered along with the mother's clinical need for CONTRAVE and any potential adverse effects on the breastfed infant from CONTRAVE or from the mother's underlying condition.

Data

In a lactation study of ten women, levels of orally dosed bupropion and its active metabolites were measured in expressed milk. The average daily infant exposure (assuming 150 mL/kg daily consumption) to bupropion and its active metabolites was 2% of the maternal weight-adjusted dose. Postmarketing reports have described seizures in breastfed infants. The relationship of bupropion exposure and these seizures is unclear.

8.4 Pediatric Use

The safety and effectiveness of CONTRAVE in pediatric patients below the age of 18 have not been established and the use of CONTRAVE is not recommended in pediatric patients.

8.5 Geriatric Use

Of the 3,239 subjects who participated in clinical trials with CONTRAVE, 62 (2%) were 65 years and older and none were 75 years and older. Clinical studies of CONTRAVE did not include sufficient numbers of subjects aged 65 and over to determine whether they respond differently from younger subjects. Older individuals may be more sensitive to the central nervous system adverse effects of CONTRAVE. Naltrexone and bupropion are known to be substantially excreted by the kidney, and the risk of adverse reactions to CONTRAVE may be greater in patients with impaired renal function. Because elderly patients are more likely to have decreased renal function, care should be taken in dose selection, and it may be useful to monitor renal function. CONTRAVE should be used with caution in patients over 65 years of age.

8.6 Renal Impairment

In a pharmacokinetic study conducted for CONTRAVE in subjects with renal impairment (mild, moderate and severe), exposure to naltrexone metabolite, 6-beta naltrexol, and bupropion metabolites, threohydrobupropion, and erythrohydrobupropion was increased. Therefore, the maximum recommended daily maintenance dose for CONTRAVE is two tablets (one tablet each morning and evening) in patients with moderate or severe renal impairment. CONTRAVE is not recommended for use in patients with end-stage renal disease [see Dosage and Administration (2.2) and Clinical Pharmacology (12.3)].

8.7 Hepatic Impairment

In a pharmacokinetic study conducted for CONTRAVE in subjects with hepatic impairment (mild, moderate, and severe), exposure to naltrexone, bupropion, and their metabolites were increased. Therefore, the maximum recommended daily maintenance dose of CONTRAVE is two tablets (one tablet each morning and evening) in patients with moderate hepatic impairment. CONTRAVE is not recommended for use in patients with severe hepatic impairment [see Dosage and Administration (2.3) and Clinical Pharmacology (12.3)].

9 DRUG ABUSE AND DEPENDENCE

9.2 Abuse

Humans

CONTRAVE has not been systematically studied in humans for its potential for abuse, tolerance, or physical dependence. However, in outpatient clinical studies of up to 56 weeks in duration, there was no evidence of euphoric drug intoxication, physical dependence, diversion, or abuse. There was no evidence of an abstinence syndrome following abrupt or tapered drug discontinuation after 56 weeks of double-blind, placebo-controlled, randomized treatment.

Naltrexone is a pure opioid antagonist. It does not lead to physical or psychological dependence. Tolerance to the opioid antagonistic effect is not known to occur.

Controlled clinical trials of bupropion (immediate-release formulation) conducted in normal volunteers, in subjects with a history of multiple drug abuse, and in depressed subjects showed some increase in motor activity and agitation/excitement. In a population of individuals experienced with drugs of abuse, a single dose of 400 mg of bupropion produced mild amphetamine-like activity as compared with placebo on the Morphine-Benzedrine Subscale of the Addiction Research Center Inventories (ARCI) and a score intermediate between placebo and amphetamine on the Liking Scale of the ARCI. These scales measure general feelings of euphoria and drug desirability.

Findings in clinical trials, however, are not known to reliably predict the abuse potential of drugs. Nonetheless, evidence from single-dose studies does suggest that the recommended daily dosage of bupropion when administered in divided doses is not likely to be significantly reinforcing to amphetamine or CNS stimulant abusers.

The inhalation of crushed tablets or injection of dissolved bupropion has been reported. Seizures and/or cases of death have been reported when bupropion has been administered intranasally or by parenteral injection. CONTRAVE (naltrexone HCl and bupropion HCl) extended-release tablets are intended for oral use only.

Animals

Studies in rodents and primates have shown that bupropion exhibits some pharmacologic actions common to psychostimulants. In rodents, it has been shown to increase locomotor activity, elicit a mild stereotyped behavioral response, and increased rates of responding in several schedule-controlled behavior paradigms. In primate models assessing the positive reinforcing effects of psychoactive drugs, bupropion was self-administered intravenously. In rats, bupropion produced amphetamine-like and cocaine-like discriminative stimulus effects in drug discrimination paradigms used to characterize the subjective effects of psychoactive drugs.

10 OVERDOSAGE

Human Experience

Overdoses of up to 30 grams or more of bupropion (equivalent of up to 83 times the recommended daily dose of CONTRAVE 32 mg/360 mg) have been reported. Seizure was reported in approximately one third of all cases. Other serious reactions reported with overdoses of bupropion alone included hallucinations, loss of consciousness, mental status changes, sinus tachycardia, ECG changes such as conduction disturbances (including QRS prolongation) or arrhythmias, clonus, myoclonus, and hyperreflexia. Fever, muscle rigidity, rhabdomyolysis, hypotension, stupor, coma, and respiratory failure have been reported mainly when bupropion was part of multiple drug overdoses.

Although most patients recovered without sequelae, deaths associated with overdoses of bupropion alone have been reported in patients ingesting large doses of the drug. Multiple uncontrolled seizures, bradycardia, cardiac failure, and cardiac arrest prior to death were reported in these patients.

Animal Experience

In the mouse, rat, and guinea pig, the oral LD50s for naltrexone were 1,100 to 1,550 mg/kg; 1,450 mg/kg; and 1,490 mg/kg; respectively. High doses of naltrexone (generally greater than or equal to 1,000 mg/kg) produced salivation, depression/reduced activity, tremors, and convulsions. Mortality in animals due to high-dose naltrexone administration usually was due to clonic-tonic convulsions and/or respiratory failure.

Overdosage Management

If over-exposure occurs, call your poison control center at 1-800-222-1222. There are no known antidotes for CONTRAVE. In case of an overdose, provide supportive care, including close medical supervision and monitoring. Consider the possibility of multiple drug overdose. Ensure an adequate airway, oxygenation, and ventilation. Monitor cardiac rhythm and vital signs. Induction of emesis is not recommended.

11 DESCRIPTION

CONTRAVE extended-release tablets contain naltrexone hydrochloride (HCl) and bupropion HCl.

Naltrexone HCl, USP, an opioid antagonist, is a synthetic congener of oxymorphone with no opioid agonist properties. Naltrexone differs in structure from oxymorphone in that the methyl group on the nitrogen atom is replaced by a cyclopropylmethyl group. Naltrexone HCl is also related to the potent opioid antagonist, naloxone, or n-allylnoroxymorphone.

Naltrexone HCl has the chemical name of morphinan-6-one, 17-(cyclopropylmethyl)-4,5-epoxy-3,14-dihydroxy-, hydrochloride, (5α)-. The empirical formula is C20H23NO4∙HCl and the molecular weight is 377.86. The structural formula is:

Naltrexone HCl is a white to yellowish, crystalline compound. It is soluble in water to the extent of about 100 mg/mL.

Bupropion HCl is an antidepressant of the aminoketone class. Bupropion HCl closely resembles the structure of diethylpropion. It is designated as (±)-1-(3 chlorophenyl)-2-[(1,1-dimethylethyl)amino]-1-propranone hydrochloride. It is related to phenylethylamines. The empirical formula is C13H18ClNO∙HCl and the molecular weight is 276.2. The structural formula is:

Bupropion HCl powder is white, crystalline, and highly soluble in water.

CONTRAVE is available for oral administration as a round, bi-convex, film-coated, extended-release tablet. Each tablet has a trilayer core composed of two drug layers, containing the drug and excipients, separated by a more rapidly dissolving inert layer. Each tablet contains 8 mg of naltrexone HCl and 90 mg of bupropion HCl. Tablets are blue and are debossed with NB-890 on one side. Each tablet contains the following inactive ingredients: microcrystalline cellulose, hydroxypropyl cellulose, lactose anhydrous, L-cysteine hydrochloride, crospovidone, magnesium stearate, hypromellose, edetate disodium, lactose monohydrate, colloidal silicon dioxide, Opadry II Blue and FD&C Blue #2 aluminum lake.

12 CLINICAL PHARMACOLOGY

12.1 Mechanism of Action

CONTRAVE has two components: naltrexone, an opioid antagonist, and bupropion, a relatively weak inhibitor of the neuronal reuptake of dopamine and norepinephrine. Nonclinical studies suggest that naltrexone and bupropion have effects on two separate areas of the brain involved in the regulation of food intake: the hypothalamus (appetite regulatory center) and the mesolimbic dopamine circuit (reward system). The exact neurochemical effects of CONTRAVE leading to weight loss are not fully understood.

12.2 Pharmacodynamics

Combined, bupropion and naltrexone increased the firing rate of hypothalamic pro-opiomelanocortin (POMC) neurons in vitro, which are associated with regulation of appetite. The combination of bupropion and naltrexone also reduced food intake when injected directly into the ventral tegmental area of the mesolimbic circuit in mice, an area associated with regulation of reward pathways.

Cardiac Electrophysiology

At the recommended dose, CONTRAVE does not prolong the QTc interval to any clinically relevant extent.

12.3 Pharmacokinetics

Absorption

Naltrexone

Following single oral administration of CONTRAVE (two 8 mg naltrexone/90 mg bupropion tablets) to healthy subjects, mean peak naltrexone concentration (Cmax) was 1.4 ng/mL, time to peak concentration (Tmax) was 2 hours, and extent of exposure (AUC0-inf) was 8.4 ng∙hr/mL.

Bupropion

Following single oral administration of CONTRAVE (two 8 mg naltrexone/90 mg bupropion tablets) to healthy subjects, mean peak bupropion concentration (Cmax) was 168 ng/mL, time to peak concentration (Tmax) was three hours, and extent of exposure (AUC0-inf) was 1,607 ng∙hr/mL.

Food Effect on Absorption

When CONTRAVE was administered with a high-fat meal, the AUC and Cmax for naltrexone increased 2.1-fold and 3.7-fold, respectively, and the AUC and Cmax for bupropion increased 1.4-fold and 1.8-fold, respectively. At steady state, the food effect increased AUC and Cmax for naltrexone by 1.7-fold and 1.9-fold, respectively, and increased AUC and Cmax for bupropion by 1.1-fold and 1.3-fold, respectively. Thus, CONTRAVE should not be taken with high-fat meals because of the resulting significant increases in bupropion and naltrexone systemic exposure.

Distribution

Naltrexone

Naltrexone is 21% plasma protein bound. The mean apparent volume of distribution at steady state for naltrexone (Vss/F) is 5,697 liters.

Bupropion

Bupropion is 84% plasma protein bound. The mean apparent volume of distribution at steady state for bupropion (Vss/F) is 880 liters.

Metabolism and Excretion

Naltrexone

The major metabolite of naltrexone is 6-beta-naltrexol. The activity of naltrexone is believed to be the result of both the parent and the 6-beta-naltrexol metabolite. Though less potent, 6-beta-naltrexol is eliminated more slowly and thus circulates at much higher concentrations than naltrexone. Naltrexone and 6-beta-naltrexol are not metabolized by cytochrome P450 enzymes and in vitro studies indicate that there is no potential for inhibition or induction of important isozymes.

Naltrexone and its metabolites are excreted primarily by the kidney (53% to 79% of the dose). Urinary excretion of unchanged naltrexone accounts for less than 2% of an oral dose. Urinary excretion of unchanged and conjugated 6-beta-naltrexol accounts for 43% of an oral dose. The renal clearance for naltrexone ranges from 30 to 127 mL/min, suggesting that renal elimination is primarily by glomerular filtration. The renal clearance for 6-beta-naltrexol ranges from 230 to 369 mL/min suggesting an additional renal tubular secretory mechanism. Fecal excretion is a minor elimination pathway.

Following single oral administration of CONTRAVE tablets to healthy subjects, mean elimination half-life (T1/2) was approximately 5 hours for naltrexone. Following twice daily administration of CONTRAVE, naltrexone did not accumulate and its kinetics appeared linear. However, in comparison to naltrexone, 6-beta-naltrexol accumulates to a larger extent (accumulation ratio ~3).

Bupropion

Bupropion is extensively metabolized with three active metabolites: hydroxybupropion, threohydrobupropion and erythrohydrobupropion. The metabolites have longer elimination half-lives than bupropion and accumulate to a greater extent. Following bupropion administration, more than 90% of the exposure is a result of metabolites. In vitro findings suggest that CYP2B6 is the principal isozyme involved in the formation of hydroxybupropion whereas cytochrome P450 isozymes are not involved in the formation of the other active metabolites. Bupropion and its metabolites inhibit CYP2D6. Plasma protein binding of hydroxybupropion is similar to that of bupropion (84%) whereas the other two metabolites have approximately half the binding.

Following oral administration of 200 mg of ^14C-bupropion in humans, 87% and 10% of the radioactive dose were recovered in the urine and feces, respectively. The fraction of the oral dose of bupropion excreted unchanged was 0.5%, a finding consistent with the extensive metabolism of bupropion.

Following single oral administration of CONTRAVE tablets to healthy subjects, mean elimination half-life (T½) was approximately 21 hours for bupropion. Following twice daily administration of CONTRAVE, metabolites of bupropion, and to a lesser extent unchanged bupropion, accumulate and reach steady-state concentrations in approximately one week.

Specific Populations

Gender

Pooled analysis of CONTRAVE data suggested no clinically meaningful differences in the pharmacokinetic parameters of bupropion or naltrexone based on gender.

Race

Pooled analysis of CONTRAVE data suggested no clinically meaningful differences in the pharmacokinetic parameters of bupropion or naltrexone based on race.

Elderly

The pharmacokinetics of CONTRAVE have not been evaluated in the geriatric population. The effects of age on the pharmacokinetics of naltrexone or bupropion and their metabolites have not been fully characterized. An exploration of steady-state bupropion concentrations from several depression efficacy studies involving patients dosed in a range of 300 to 750 mg/day, on a three times daily schedule, revealed no relationship between age (18 to 83 years) and plasma concentration of bupropion. A single-dose pharmacokinetic study demonstrated that the disposition of bupropion and its metabolites in elderly subjects was similar to that of younger subjects. These data suggest there is no prominent effect of age on bupropion concentration; however, another pharmacokinetic study, single and multiple dose, has suggested that the elderly are at increased risk for accumulation of bupropion and its metabolites [see Use in Specific Populations (8.5)].

Smokers

Pooled analysis of CONTRAVE data revealed no meaningful differences in the plasma concentrations of bupropion or naltrexone in smokers compared with nonsmokers. The effects of cigarette smoking on the pharmacokinetics of bupropion were studied in 34 healthy male and female volunteers; 17 were chronic cigarette smokers and 17 were nonsmokers. Following oral administration of a single 150 mg dose of bupropion, there was no statistically significant difference in Cmax, half-life, Tmax, AUC, or clearance of bupropion or its active metabolites between smokers and nonsmokers.

Hepatic Impairment

A single dose pharmacokinetic study conducted for CONTRAVE, comparing patients with mild (n=8), moderate (n=8) and severe (n=7) hepatic impairment based on CHILD-PUGH classification system to subjects with normal hepatic function (n=13), showed that hepatic impairment had a significant effect on the PK parameters of the parent drugs naltrexone and bupropion. Systemic exposure to some metabolites was also increased in patients with impaired hepatic function [see Dosage and Administration (2.3) and Use in Specific Populations (8.7)].

Following a single dose of naltrexone/bupropion, AUCinf of naltrexone was approximately 2.8-, 6.1-, and 34-fold higher in patients with mild, moderate, and severe hepatic impairment, respectively. In patients with moderate and severe hepatic impairment, AUCinf of bupropion was approximately 2.0- and 3.6-fold higher, respectively, compared to subjects with normal hepatic function. There was no effect of mild hepatic impairment on bupropion exposure. Exposure to bupropion metabolite, threohydrobupropion, was increased by 1.9-, 3.4-, and 2.5-fold in patients with mild, moderate, and severe hepatic impairment, respectively [see Dosage and Administration (2.3) and Use in Specific Populations (8.7)].

Renal Impairment

A single-dose pharmacokinetic study conducted for CONTRAVE, comparing patients with mild (n=8), moderate (n=8) and severe (n=7) renal impairment to subjects with normal renal function (n=13), showed that renal impairment had no significant effect on the PK parameters of the parent drugs naltrexone and bupropion. However, systemic exposure (AUCinf) of some metabolites was increased in patients with impairment of renal function [see Dosage and Administration (2.2) and Use in Specific Populations (8.6)].

Following a single-dose of 16 mg naltrexone /180 mg bupropion, AUCinf of 6-beta-naltrexol was approximately1.5-, 1.7-, and 2.2-fold higher in patients with mild, moderate, and severe renal impairment, respectively. In patients with mild, moderate, and severe renal impairment, AUC of bupropion metabolites threohydrobupropion and erythrohydrobupropion increased approximately 1.3-, 1.9-, and 1.7-fold and 1.2-, 1.8-, and 1.5-fold, respectively. No studies have been conducted for CONTRAVE in patients with end stage renal disease.

The following information is available for individual components.

In a study of seven patients with end-stage renal disease requiring dialysis, peak plasma concentrations of naltrexone were elevated at least 6-fold compared to healthy subjects. An inter-trial comparison between normal subjects and patients with end-stage renal failure demonstrated that the bupropion Cmax and AUC values were comparable in the two groups, whereas the hydroxybupropion and threohydrobupropion metabolites had a 2.3- and 2.8-fold increase, respectively, in AUC for patients with end-stage renal failure.

Drug Interactions

In Vitro Assessment of Drug Interactions

At therapeutically relevant concentrations, naltrexone and 6-beta-naltrexol are not major inhibitors of CYP isoforms CYP1A2, CYP2B6, CYP2C8, CYP2E1, CYP2C9, CYP2C19, CYP2D6 or CYP3A4. Both naltrexone and 6-beta-naltrexol are not major inducers of CYP isoforms CYP1A2, CYP2B6, or CYP3A4.

Bupropion and its metabolites (hydroxybupropion, erythrohydrobupropion, threohydrobupropion) are inhibitors of CYP2D6.

In vitro studies suggest that paroxetine, sertraline, norfluoxetine, fluvoxamine, and nelfinavir inhibit the hydroxylation of bupropion.

Bupropion (IC50 9.3 mcM) and its metabolites, hydroxybupropion (IC50 82 mcM) and threohydrobupropion and erythrohydrobupropion (1:1 mixture; IC50 7.8 mcM), inhibited the renal organic transporter OCT2 to a clinically relevant level.

Effects of Naltrexone/Bupropion on the Pharmacokinetics of Other Drugs

Drug interaction between CONTRAVE and CYP2D6 substrates (metoprolol) or other drugs (atorvastatin, glyburide, lisinopril, nifedipine, valsartan) has been evaluated. In addition, drug interaction between bupropion, a component of CONTRAVE, and CYP2D6 substrates (desipramine) or other drugs (citalopram, lamotrigine) has also been evaluated.

Table 4. Effect of Naltrexone/Bupropion Coadministration on Systemic Exposure of Other Drugs
Naltrexone/Bupropion Dosage | Coadministered Drug
Naltrexone/Bupropion Dosage | Name and Dose Regimens | Change in Systemic Exposure
Initiate the following drugs at the lower end of the dose range during concomitant use with CONTRAVE [see Drug Interactions 7]:
Bupropion 150 mg twice daily for 10 days | Desipramine 50 mg single dose | ↑5-fold AUC, ↑2-fold Cmax
Bupropion 300 mg (as XL) once daily for 14 days | Citalopram 40 mg once daily for 14 days | ↑40% AUC, ↑30% Cmax
Naltrexone/Bupropion 16 mg/180 mg twice daily for 7 days | Metoprolol 50 mg single dose | ↑4-fold AUC, ↑2-fold Cmax
No dose adjustment needed for the following drugs during concomitant use with CONTRAVE:
Naltrexone/Bupropion 16 mg/180 mg single dose | Atorvastatin 80 mg single dose | No Effect
Naltrexone/Bupropion 16 mg/180 mg single dose | Glyburide 6 mg single dose | No Effect
Naltrexone/Bupropion 16 mg/180 mg single dose | Lisinopril 40 mg single dose | No Effect
Naltrexone/Bupropion 16 mg/180 mg twice daily | Metformin 850 mg single dose | ↑23% AUC; No effect on Cmax
Naltrexone/Bupropion 16 mg/180 mg single dose | Nifedipine 90 mg single dose | No Effect
Naltrexone/Bupropion 16 mg/180 mg single dose | Valsartan 320 mg single dose | No Effect
Bupropion 150 mg twice daily for 12 days | Lamotrigine 100 mg single dose | No Effect

Digoxin: Literature data showed that digoxin exposure was decreased when a single oral dose of 0.5 mg digoxin was administered 24 hours after a single oral dose of extended-release 150 mg bupropion in healthy volunteers.

Effects of Other Drugs on the Pharmacokinetics of Naltrexone/Bupropion

Drug interactions between CYP2B6 inhibitors (ticlopidine, clopidogrel, prasugrel), CYP2B6 inducers (ritonavir, lopinavir) and bupropion (one of the CONTRAVE components), or between other drugs (atorvastatin, glyburide, metoprolol, lisinopril, nifedipine, valsartan) and CONTRAVE have been evaluated. While not systematically studied, carbamazepine, phenobarbital, or phenytoin may induce the metabolism of bupropion.

Table 5. Effect of Coadministered Drugs on Systemic Exposure of Naltrexone/Bupropion
Name and Dose Regimens | Coadministered Drug
Name and Dose Regimens | CONTRAVE Components | Change in Systemic Exposure
Do not exceed one tablet twice daily dose of CONTRAVE with the following drugs:
Ticlopidine 250 mg twice daily for 4 days | Bupropion Hydroxybupropion | ↑85% AUC, ↑38% Cmax ↓84% AUC, ↓78% Cmax
Clopidogrel 75 mg once daily for 4 days | Bupropion Hydroxybupropion | ↑60% AUC, ↑40% Cmax ↓52% AUC, ↓50% Cmax
No dose adjustment needed for CONTRAVE with the following drugs:
Atorvastatin 80 mg single dose | Naltrexone 6-beta naltrexol Bupropion Hydroxybupropion Threohydrobupropion Erythrohydrobupropion | No Effect No Effect No Effect No Effect No Effect No Effect
Lisinopril 40 mg single dose | Naltrexone 6-beta naltrexol Bupropion Hydroxybupropion Threohydrobupropion Erythrohydrobupropion | No Effect No Effect No Effect No Effect No Effect No Effect
Valsartan 320 mg single dose | Naltrexone 6-beta naltrexol Bupropion Hydroxybupropion Threohydrobupropion Erythrohydrobupropion | No Effect No Effect No Effect ↓14% AUC, No Effect on Cmax No Effect No Effect
Cimetidine 800 mg single dose | Bupropion Hydroxybupropion Threo/Erythrohydrobupropion | No Effect No Effect ↑16% AUC, ↑32% Cmax
Citalopram 40 mg once daily for 14 days | Bupropion Hydroxybupropion Threohydrobupropion Erythrohydrobupropion | No Effect No Effect No Effect No Effect
Metoprolol 50 mg single dose | Naltrexone 6-beta naltrexol Bupropion Hydroxybupropion Threohydrobupropion Erythrohydrobupropion | ↓25% AUC, ↓29% Cmax No Effect No Effect No Effect No Effect No Effect
Metformin 850 mg single dose | Bupropion Hydroxybupropion Threohydrobupropion Erythrohydrobupropion Naltrexone 6-beta naltrexol | No Effect No Effect No Effect No Effect No Effect No Effect
Nifedipine 90 mg single dose | Naltrexone 6-beta naltrexol Bupropion Hydroxybupropion Threohydrobupropion Erythrohydrobupropion | ↑24% AUC, ↑58% Cmax No Effect No Effect on AUC, ↑22% Cmax No Effect No Effect No Effect
Prasugrel 10 mg once daily for 6 days | Bupropion Hydroxybupropion | ↑18% AUC, ↑14% Cmax ↓24%AUC, ↓32% Cmax
Use CONTRAVE with caution with the following drugs:
Glyburide 6 mg single dose [Results were confounded by the food-effect due to oral glucose coadministered with the treatment.] | Naltrexone 6-beta naltrexol Bupropion Hydroxybupropion Threohydrobupropion Erythrohydrobupropion | ↑2-fold AUC, ↑2-fold Cmax No Effect ↑36% AUC, ↑18% Cmax ↑22% AUC, ↑21% Cmax No Effect on AUC, ↑15% Cmax No Effect
Avoid concomitant use of CONTRAVE with following drugs:
Ritonavir 100 mg twice daily for 17 days | Bupropion Hydroxybupropion Threohydrobupropion Erythrohydrobupropion | ↓22% AUC, ↓21 % Cmax ↓23% AUC, No Effect on Cmax ↓38% AUC, ↓39 % Cmax ↓48% AUC, ↓28 % Cmax
600 mg twice daily for 8 days | Bupropion Hydroxybupropion Threohydrobupropion Erythrohydrobupropion | ↓66% AUC, ↓62% Cmax ↓78% AUC, ↓42 % Cmax ↓50% AUC, ↓58% Cmax ↓68% AUC, ↓48 % Cmax
Lopinavir/Ritonavir 400 mg/100 mg twice daily for 14 days | Bupropion Hydroxybupropion | ↓57% AUC, ↓57% Cmax ↓50% AUC, ↓31% Cmax
Efavirenz 600 mg once daily for 2 weeks | Bupropion Hydroxybupropion | ↓55% AUC, ↓34% Cmax No Effect on AUC, ↑50% Cmax

13 NONCLINICAL TOXICOLOGY

13.1 Carcinogenesis, Mutagenesis, Impairment of Fertility

Studies to evaluate carcinogenesis, mutagenesis, or impairment of fertility with the combined products in CONTRAVE have not been conducted. The following findings are from studies performed individually with naltrexone and bupropion. The potential carcinogenic, mutagenic and fertility effects of the metabolite 6-beta-naltrexol are unknown. Safety margins were estimated using body surface area exposure (mg/m^2) based on a body weight of 100 kg.

In a two-year carcinogenicity study in rats with naltrexone, there were small increases in the numbers of testicular mesotheliomas in males and tumors of vascular origin in males and females. The incidence of mesothelioma in males given naltrexone at a dietary dose of 100 mg/kg/day (approximately 50 times the recommended therapeutic dose on a mg/m^2 basis for the naltrexone maintenance dose for CONTRAVE) was 6%, compared with a maximum historical incidence of 4%. The incidence of vascular tumors in males and females given dietary doses of 100 mg/kg/day was 4%, but only the incidence in females was increased compared with a maximum historical control incidence of 2%. There was no evidence of carcinogenicity in a two-year dietary study with naltrexone in male and female mice.

Lifetime carcinogenicity studies of bupropion were performed in rats and mice at doses up to 300 and 150 mg/kg/day, respectively. These doses are approximately 14 and 3 times the maximum recommended human dose (MRHD) of the bupropion component in CONTRAVE, respectively, on a mg/m^2 basis. In the rat study there was an increase in nodular proliferative lesions of the liver at doses of 100 to 300 mg/kg/day (approximately 5 to 14 times the MRHD of the bupropion component in CONTRAVE on a mg/m^2 basis); lower doses were not tested. The question of whether or not such lesions may be precursors of neoplasms of the liver is currently unresolved. Similar liver lesions were not seen in the mouse study, and no increase in malignant tumors of the liver and other organs was seen in either study.

There was limited evidence of a weak genotoxic effect of naltrexone in one gene mutation assay in a mammalian cell line, in the Drosophila recessive lethal assay, and in non-specific DNA repair tests with E. coli. However, no evidence of genotoxic potential was observed in a range of other in vitro tests, including assays for gene mutation in bacteria, yeast, or in a second mammalian cell line, a chromosomal aberration assay, and an assay for DNA damage in human cells. Naltrexone did not exhibit clastogenicity in an in vivo mouse micronucleus assay.

Bupropion produced a positive response (two to three times control mutation rate) in two of five strains in the Ames bacterial mutagenicity test and an increase in chromosomal aberrations in one of three in vivo rat bone marrow cytogenetic studies.

Naltrexone administered orally to rats caused a significant increase in pseudopregnancy and a decrease in pregnancy rates in rats at 100 mg/kg/day (approximately 50 times the MRHD of the naltrexone component in CONTRAVE on a mg/m^2 basis). There was no effect on male fertility at this dose level. The relevance of these observations to human fertility is not known.

A fertility study of bupropion in rats at doses up to 300 mg/kg/day (approximately 14 times the MRHD of the bupropion component in CONTRAVE on a mg/m^2 basis) revealed no evidence of impaired fertility.

14 CLINICAL STUDIES

The effects of CONTRAVE on weight reduction and long-term maintenance in conjunction with reduced caloric intake and increased physical activity was studied in double-blind, placebo-controlled trials (BMI range 27 to 45 kg/m^2) with study durations of 16 to 56 weeks randomized to naltrexone and/or bupropion or placebo.

Effect on Weight Reduction and Long-Term Maintenance

Four 56-week multicenter, double-blind, placebo-controlled obesity trials (CONTRAVE Obesity Research, or COR-I, COR-II, COR-BMOD, and COR-Diabetes) were conducted to evaluate the effect of CONTRAVE on weight reduction in conjunction with lifestyle modification in 4,536 patients randomized to CONTRAVE or placebo. The COR-I, COR-II, and COR-BMOD trials enrolled patients with obesity (BMI 30 kg/m^2 or greater) or overweight (BMI 27 kg/m^2 or greater) and at least one comorbidity (hypertension or dyslipidemia). The COR-Diabetes trial enrolled patients with BMI greater than 27 kg/m^2 with type 2 diabetes with or without hypertension and/or dyslipidemia.

Treatment was initiated with a three-week dose-escalation period followed by approximately 1 year of continued therapy. Patients were instructed to take CONTRAVE with food. COR-I and COR-II included a program consisting of a reduced-calorie diet resulting in an approximate 500 kcal/day decrease in caloric intake, behavioral counseling, and increased physical activity. COR-BMOD included an intensive behavioral modification program consisting of 28 group counseling sessions over 56 weeks as well as a prescribed diet and exercise regimen. COR-Diabetes evaluated patients with type 2 diabetes not achieving glycemic goal of a HbA1c less than 7% either with oral antidiabetic agents or with diet and exercise alone. Of the overall population from these four trials, 24% had hypertension, 54% had dyslipidemia at study entry, and 10% had type 2 diabetes.

Apart from COR-Diabetes, which only enrolled patients with type 2 diabetes, the demographic characteristics of patients were similar across all four trials. For the four trial populations combined, the mean age was 46 years, 83% were female, 77% were Caucasian, 18% were black, and 5% were other races. At baseline, mean BMI was 36 kg/m^2 and mean waist circumference was 110 cm.

A substantial percentage of randomized patients withdrew from the trials prior to Week 56: 45% for the placebo group and 46% for the CONTRAVE group. The majority of these patients discontinued within the first 12 weeks of treatment. Approximately 24% of patients treated with CONTRAVE and 12% of patients treated with placebo discontinued treatment because of an adverse reaction [see Adverse Reactions (6.1)].

The co-primary endpoints were percent change from baseline body weight and the proportion of patients achieving at least a 5% reduction in body weight. In the 56-week COR-I trial, the mean change in body weight was -5.4% among patients assigned to CONTRAVE 32 mg/360 mg compared with -1.3% among patients assigned to placebo (Intent-To-Treat [ITT] population), as shown in Table 6 and Figure 1. In this trial, the achievement of at least a 5% reduction in body weight from baseline occurred more frequently for patients treated with CONTRAVE 32 mg/360 mg compared with placebo (42% vs 17%; Table 6). Results from COR-BMOD and COR-Diabetes are shown in Table 6 and Figures 2 and 3.

Table 6. Changes in Weight in 56-Week Trials with CONTRAVE (ITT/LOCF [Based on last observation carried forward (LOCF) in all randomized subjects who had a baseline body weight measurement and at least one post baseline body weight measurement during the defined treatment phase. All available body weight data during the double-blind treatment phase are included in the analysis, including data collected from subjects who discontinued study drug.])
 | COR-I |  | COR-BMOD |  | COR-Diabetes
 | CONTRAVE 32 mg/360 mg | Placebo | CONTRAVE 32 mg/360 mg | Placebo | CONTRAVE 32 mg/360 mg | Placebo
N | 538 | 536 | 565 | 196 | 321 | 166
Weight (kg)
Baseline mean (SD) | 99.8 (16.1) | 99.5 (14.4) | 100.3 (15.5) | 101.8 (15.0) | 104.2 (19.1) | 105.3 (16.9)
LS Mean % Change From Baseline (SE) | -5.4 (0.3) | -1.3 (0.3) | -8.1 (0.4) | -4.9 (0.6) | -3.7 (0.3) | -1.7 (0.4)
Difference from placebo (95% CI) | -4.1 [Difference from placebo, p<0.001] (-4.9, -3.3) |  | -3.2 (-4.5, -1.8) |  | -2.0 (-3.0, -1.0)
Percentage of patients losing greater than or equal to 5% body weight | 42 | 17 | 57 | 43 | 36 | 18
Risk difference vs placebo (95% CI) | 25 (19, 30) |  | 14 (6, 22) |  | 18 (9, 25)
Percentage of patients losing greater than or equal to 10% body weight | 21 | 7 | 35 | 21 | 15 | 5
Risk difference vs placebo (95% CI) | 14 (10, 18) |  | 14 (7, 21) |  | 10 [Difference from placebo, p<0.01] (4, 15)
Type 1 error was controlled across all 3 endpoints

The percentages of patients who achieved at least 5% or at least 10% body weight loss from baseline were greater among those assigned to CONTRAVE, compared with placebo, in all four obesity trials (Table 6).

Figure 1. Weight Loss Over Time in Completer Population: COR-I Trial

Figure 2. Weight Loss Over Time in Completer Population: COR-BMOD Trial

*p<0.001 vs placebo
COR-I trial: 50.1% in the placebo group and 49.2% in the CONTRAVE group discontinued study drug.

*p<0.001 vs placebo COR-BMOD trial: 41.6% in the placebo group and 42.1% in the CONTRAVE group discontinued study drug.

Figure 3. Weight Loss Over Time in Completer Population: COR-Diabetes Trial

*p<0.001 vs placebo
COR-Diabetes trial: 41.2% in the placebo group and 47.8% in the CONTRAVE group discontinued study drug.

Effect on Cardiovascular and Metabolic Parameters

Changes in cardiovascular and metabolic parameters associated with obesity are presented for COR-I and COR-BMOD (Table 7). Changes in mean blood pressure and heart rate are further described elsewhere [see Warnings and Precautions (5.5)].

Table 7. Change in Markers of Cardiovascular and Metabolic Parameters from Baseline in 56 Week Trials with CONTRAVE 32 mg/360 mg (COR-I and COR-BMOD) [Based on last observation carried forward (LOCF) while on study drug]
Parameter | COR-I |  |  | COR-BMOD
 | CONTRAVE 32 mg/360 mg N=471 | Placebo N=511 | CONTRAVE minus Placebo (LS Mean) | CONTRAVE 32 mg/360 mg N=482 | Placebo N=193 | CONTRAVE minus Placebo (LS Mean)
Triglycerides, mg/dL
Baseline median (Q1, Q3) | 113 (86, 158) | 112 (78, 157) | -10.7 [Hodges-Lehmann estimate of treatment difference] | 110 (78, 162) | 103 (76, 144) | -9.9
Median % change | -11.6 | 1.7 | -10.7 [Hodges-Lehmann estimate of treatment difference] | -17.8 | -7.4 | -9.9
HDL-C, mg/dL
Baseline mean (SD) | 51.9 (13.6) | 52.0 (13.6) | 7.2 | 53.6 (13.5) | 55.3 (12.9) | 6.6
LS Mean % change (SE) | 8.0 (0.9) | 0.8 (0.9) | 7.2 | 9.4 (1.0) | 2.8 (1.6) | 6.6
LDL-C, mg/dL
Baseline mean (SD) | 118.8 (32.6) | 119.7 (34.8) | -1.5 | 109.5 (27.5) | 109.2 (27.3) | -2.9
LS Mean % change (SE) | -2.0 (1.0) | -0.5 (1.1) | -1.5 | 7.1 (1.4) | 10.0 (2.2) | -2.9
Waist circumference, cm
Baseline mean (SD) | 108.8 (11.3) | 110.0 (12.2) | -3.8 [Statistically significant vs placebo (p<0.001) based on the pre-specified closed testing procedure method for controlling Type I error] | 109.3 (11.4) | 109.0 (11.8) | -3.2
LS Mean change (SE) | -6.2 (0.4) | -2.5 (0.4) | -3.8 [Statistically significant vs placebo (p<0.001) based on the pre-specified closed testing procedure method for controlling Type I error] | -10.0 (0.5) | -6.8 (0.8) | -3.2
Heart rate, bpm
Baseline mean (SD) | 72.1 (8.7) | 71.8 (8.0) | 1.2 | 70.7 (8.3) | 70.4 (9.0) | 0.9
LS Mean change (SE) | 1.0 (0.3) | -0.2 (0.3) | 1.2 | 1.1 (0.4) | 0.2 (0.5) | 0.9
Systolic blood pressure, mmHg
Baseline mean (SD) | 118.9 (9.8) | 119.0 (9.8) | 1.8 | 116.9 (9.9) | 116.7 (10.9) | 2.6
LS Mean change (SE) | -0.1 (0.4) | -1.9 (0.4) | 1.8 | -1.3 (0.5) | -3.9 (0.7) | 2.6
Diastolic blood pressure, mmHg
Baseline mean (SD) | 77.1 (7.2) | 77.3 (6.6) | 0.9 | 78.2 (7.2) | 77.2 (7.4) | 1.4
LS Mean change (SE) | 0.0 (0.3) | -0.9 (0.3) | 0.9 | -1.4 (0.3) | -2.8 (0.5) | 1.4
Q1: first quartile; Q3: third quartile

Effect of CONTRAVE on Cardiometabolic Parameters and Anthropometry in Patients with Type 2 Diabetes Mellitus

Changes in glycemic control observed from baseline to Week 56 among patients with type 2 diabetes and obesity assigned to either CONTRAVE 32 mg/360 mg or placebo are shown in Table 8.

Table 8. Changes in Cardiometabolic Parameters and Waist Circumference in Patients with Type 2 Diabetes Mellitus in a 56 Week Trial with CONTRAVE 32 mg/360 mg (COR-Diabetes)
 | CONTRAVE 32 mg/360 mg N=265 |  | Placebo N=159
 | Baseline | Change from Baseline (LS Mean) | Baseline | Change from Baseline (LS Mean) | CONTRAVE minus Placebo (LS Mean)
HbA1c (%) | 8.0 | -0.6 | 8.0 | -0.1 | -0.5 [Statistically significant vs placebo (p<0.001) based on the pre-specified closed testing procedure method for controlling Type I error]
Fasting Glucose (mg/dL) | 160.0 | -11.9 | 163.9 | -4.0 | -7.9
Waist Circumference (cm) | 115.6 | -5.0 | 114.3 | -2.9 | -2.1
Systolic blood pressure (mmHg) | 125.0 | 0.0 | 124.5 | -1.1 | 1.2
Diastolic blood pressure (mmHg) | 77.5 | -1.1 | 77.4 | -1.5 | 0.4
Heart rate (bpm) | 72.9 | 0.7 | 73.1 | -0.2 | 0.9
 | Baseline | % Change from Baseline (LS Mean) | Baseline | % Change from Baseline (LS Mean) | CONTRAVE minus Placebo (LS Mean)
Triglycerides (mg/dL) [Values are baseline median (first and third quartiles), median % change, and the Hodges-Lehmann estimate of the median treatment difference] | 147 (98, 200) | -7.7 | 168 (114, 236) | -8.6 | -3.3
HDL Cholesterol (mg/dL) | 46.2 | 7.4 | 46.1 | -0.2 | 7.6
LDL Cholesterol (mg/dL) | 100.2 | 2.4 | 101.0 | 4.2 | -1.9
Based on last observation carried forward (LOCF) while on study drug

Effect on Body Composition

In a subset of 124 patients (79 CONTRAVE, 45 placebo), body composition was measured using dual energy X-ray absorptiometry (DEXA). The DEXA assessment showed that mean total body fat mass decreased by 4.7 kg (11.7%) in the CONTRAVE group vs 1.4 kg (4.3%) in the placebo group at Week 52/LOCF (treatment difference, -3.3 kg [-7.4%], p<0.01).

16 HOW SUPPLIED/STORAGE AND HANDLING

CONTRAVE 8 mg/90 mg (naltrexone HCl 8 mg and bupropion HCl 90 mg) extended-release tablets are blue, round, bi-convex, film-coated tablets debossed with "NB-890" on one side. CONTRAVE tablets are available as follows:

 | NDC 51267-890-99 | Bottles of 120 tablets

Storage

Store at 25°C (77°F); excursions permitted to 15° to 30°C (59° to 86°F) [see USP Controlled Room Temperature].

17 PATIENT COUNSELING INFORMATION

Advise the patient to read the FDA-approved patient labeling (Medication Guide)

Patient information is printed at the end of this insert. This information and the instructions provided in the Medication Guide should be discussed with patients.

Patients should be advised to take CONTRAVE exactly as prescribed. Patients should be instructed to follow the dose escalation schedule and not to take more than the recommended dose of CONTRAVE.

Patients should be made aware that CONTRAVE contains the same active ingredient (bupropion) found in certain antidepressants and smoking cessation products (including, but not limited to, WELLBUTRIN, WELLBUTRIN SR, WELLBUTRIN XL, APLENZIN and ZYBAN) and that CONTRAVE should not be used in combination with any other medications that contain bupropion.

Patients should be advised that some patients have experienced changes in mood (including depression and mania), psychosis, hallucinations, paranoia, delusions, homicidal ideation, aggression, hostility, agitation, anxiety, and panic, as well as suicidal ideation, suicide attempt, and completed suicide when attempting to quit smoking while taking bupropion. Instruct patients to discontinue CONTRAVE and contact a healthcare professional if they experience such symptoms.

Patients should be advised of the potential serious risks associated with the use of CONTRAVE, including suicidality, seizures, and increases in blood pressure or heart rate.

Patients should be advised to call their healthcare provider to report new or sudden changes in mood, behavior, thoughts, or feelings.

Patients should be advised that taking CONTRAVE can cause mild pupillary dilation, which in susceptible individuals, can lead to an episode of angle-closure glaucoma. Pre-existing glaucoma is almost always open-angle glaucoma because angle-closure glaucoma, when diagnosed, can be treated definitively with iridectomy. Open-angle glaucoma is not a risk factor for angle-closure glaucoma. Patients may wish to be examined to determine whether they are susceptible to angle closure, and have a prophylactic procedure (e.g., iridectomy), if they are susceptible.

Patients should be educated on the symptoms of hypersensitivity and to discontinue CONTRAVE if they have a severe allergic reaction to CONTRAVE.

Patients should be told that CONTRAVE should be discontinued and not restarted if they experience a seizure while on treatment.

Patients should be advised that the excessive use or abrupt discontinuation of alcohol, benzodiazepines, antiepileptic drugs, or sedatives/hypnotics can increase the risk of seizure. Patients should be advised to minimize or avoid use of alcohol.

Patients should be advised that if they previously used opioids, they may be more sensitive to lower doses of opioids and at risk of accidental overdose should they use opioids after CONTRAVE treatment is discontinued or temporarily interrupted.

Patients should be advised that because naltrexone, a component of CONTRAVE, can block the effects of opioids, they will not perceive any effect if they attempt to self-administer any opioid drug in small doses while on CONTRAVE. Further advise patients that the attempt to administer large doses of any opioid or to bypass the blockade while on CONTRAVE may lead to serious injury, coma, or death.

Patients should be off all opioids for a minimum of 7 to 10 days before starting CONTRAVE in order to avoid precipitation of withdrawal. Advise patients they should not take CONTRAVE if they have any symptoms of opioid withdrawal.

Patients should be advised to call their healthcare provider if they experience increased blood pressure or heart rate.

Patients should be advised to notify their healthcare provider if they are taking, or plan to take, any prescription or over-the-counter drugs. Concern is warranted because CONTRAVE and other drugs may affect each other's metabolism.

Pregnancy

Advise pregnant patients and all patients who can become pregnant of the potential risk to a fetus. Advise patients to inform their healthcare provider of a known or suspected pregnancy to discuss if CONTRAVE should be discontinued [see Use in Specific Populations (8.1)].

Patients with type 2 diabetes mellitus on antidiabetic therapy should be advised to monitor their blood glucose levels and report symptoms of hypoglycemia to their healthcare provider(s).

Patients should be advised to swallow CONTRAVE tablets whole so that the release rate is not altered. Do not chew, divide, or crush tablets.

Distributed by:

Currax™ Pharmaceuticals LLC,

Brentwood, TN 37027

CONTRAVE® is a registered trademark of Nalpropion Pharmaceuticals LLC

All other trademarks are the property of their respective owners.

© 2025 Nalpropion Pharmaceuticals LLC

MEDICATION GUIDE
CONTRAVE® (CON-trayv)
(naltrexone HCl and bupropion HCl) extended-release tablets

What is the most important information I should know about CONTRAVE?

CONTRAVE can cause serious side effects, including:

- Suicidal thoughts or actions. One of the ingredients in CONTRAVE is bupropion. Bupropion has caused some people to have suicidal thoughts or actions or unusual changes in behavior, whether or not they are taking medicines used to treat depression.
  Bupropion may increase suicidal thoughts or actions in some children, teenagers, and young adults within the first few months of treatment.
  If you already have depression or other mental illnesses, taking bupropion may cause it to get worse, especially within the first few months of treatment.
  Stop taking CONTRAVE and call a healthcare provider right away if you, or your family member, have any of the following symptoms, especially if they are new, worse, or worry you:

- thoughts about suicide or dying
- attempts to commit suicide
- new or worse depression
- new or worse anxiety
- feeling very agitated or restless
- panic attacks

- new or worse irritability
- acting aggressive, being angry, or violent
- acting on dangerous impulses
- an extreme increase in activity and talking (mania)
- other unusual changes in behavior or mood
- trouble sleeping (insomnia)

While taking CONTRAVE, you or your family members should:

- Pay close attention to any changes, especially sudden changes, in mood, behaviors, thoughts, or feelings. This is very important when you start taking CONTRAVE or when your dose changes.
- Keep all follow-up visits with your healthcare provider as scheduled. Call your healthcare provider between visits as needed, especially if you have concerns about symptoms.

CONTRAVE has not been studied in and is not approved for use in children under the age of 18.

What is CONTRAVE?

CONTRAVE is a prescription medicine which contains 2 medicines (naltrexone and bupropion) that may help adults with obesity, or some adults with overweight who also have weight-related medical problems, to lose excess body weight and keep the weight off.

CONTRAVE should be used with a reduced calorie-diet and increased physical activity.

It is not known if CONTRAVE changes your risk of heart problems or stroke or of death due to heart problems or stroke.

It is not known if CONTRAVE is safe and effective in children under 18 years of age.

CONTRAVE contains naltrexone and bupropion and should not be used with other products that contain naltrexone or bupropion. Bupropion is the same ingredient in some other medicines used to treat depression and to help people quit smoking. CONTRAVE is not approved to treat depression or other mental illnesses, or to help people quit smoking (smoking cessation)

Do not take CONTRAVE if you:

- have uncontrolled hypertension.
- have or have had seizures.
- use other medicines that contain bupropion such as WELLBUTRIN, WELLBUTRIN SR, WELLBUTRIN XL, APLENZIN and ZYBAN.
- have or have had an eating disorder called anorexia (eating very little) or bulimia (eating too much and vomiting to avoid gaining weight).
- are dependent on opioid pain medicines or use medicines to help stop taking opioids such as methadone or buprenorphine, or are in opiate withdrawal.
- drink a lot of alcohol and abruptly stop drinking, or use medicines called sedatives (these make you sleepy), benzodiazepines, or anti-seizure medicines and you stop using them all of a sudden.
- are taking medicines called monoamine oxidase inhibitors (MAOIs). Ask your healthcare provider or pharmacist if you are not sure if you take an MAOI, including linezolid. Do not start CONTRAVE until you have stopped taking your MAOI for at least 14 days.
- are allergic to naltrexone or bupropion or any of the ingredients in CONTRAVE. See the end of this Medication Guide for a complete list of ingredients in CONTRAVE.

Before taking CONTRAVE, tell your healthcare provider about all of your medical conditions, including if you:

- have or have had depression or other mental illnesses (such as bipolar disorder)
- have attempted suicide in the past
- have or have had seizures
- have had a head injury
- have had a tumor or infection of your brain or spine (central nervous system)
- have had a problem with low blood sugar (hypoglycemia) or low levels of sodium in your blood (hyponatremia)
- have or have had liver problems
- have high blood pressure
- have or have had a heart attack, heart problems, or have had a stroke
- have kidney problems
- are diabetic taking insulin or other medicines to control your blood sugar
- have or have had an eating disorder
- drink a lot of alcohol
- abuse prescription medicines or street drugs
- are over the age of 65
- are pregnant or plan to become pregnant. Losing weight while pregnant may harm your unborn baby. Stop taking CONTRAVE if you become pregnant. Tell your healthcare provider if you become pregnant or you think you may be pregnant during treatment with CONTRAVE.
- are breastfeeding or plan to breastfeed. CONTRAVE can pass into your breast milk and may harm your baby. You and your healthcare provider should decide if you should take CONTRAVE or breastfeed. You should not do both.

Tell your healthcare provider about all the medicines you take, including prescription and over-the-counter medicines, vitamins, and herbal supplements.

CONTRAVE may affect the way other medicines work and other medicines may affect the way CONTRAVE works causing side effects.

Ask your healthcare provider for a list of these medicines if you are not sure.

Know the medicines you take. Keep a list of them to show your healthcare provider or pharmacist when you get a new medicine.

How should I take CONTRAVE?

How to take CONTRAVE

Morning Dose

Evening Dose

Starting: Week 1

1 tablet

None

Week 2

1 tablet

1 tablet

Week 3

2 tablets

1 tablet

Week 4 Onward

2 tablets

2 tablets

- Take CONTRAVE exactly as your healthcare provider tells you to.
- If you have kidney or liver problems, your final dose may be lower (for example, one tablet in the morning and one tablet in the evening or one tablet in the morning).
- Your healthcare provider will change your dose if needed.
- Do not change your CONTRAVE dose without talking with your healthcare provider.
- Your healthcare provider should tell you to stop taking CONTRAVE if you have not lost a certain amount of weight after 16 weeks of treatment.
- Swallow CONTRAVE tablets whole. Do not cut, chew, or crush CONTRAVE tablets. Tell your healthcare provider if you cannot swallow CONTRAVE tablets whole.
- Do not take more than 2 tablets in the morning and 2 tablets in the evening.
- Do not take more than 2 tablets at the same time or more than 4 tablets in 1 day.
- Do not take CONTRAVE with high-fat meals. It may increase your risk of seizures.
- If you miss a dose of CONTRAVE, wait until your next regular time to take it. Do not take more than 1 dose of CONTRAVE at a time.
- If you take too much CONTRAVE, call your healthcare provider or your poison control center at 1-800-222-1222 right away, or go to the nearest emergency room.

What should I avoid while taking CONTRAVE?

- Do not drink a lot of alcohol while taking CONTRAVE. If you drink a lot of alcohol, talk with your healthcare provider before suddenly stopping. If you suddenly stop drinking alcohol, you may increase your chance of having a seizure.

What are the possible side effects of CONTRAVE?

CONTRAVE may cause serious side effects, including:

- See "What is the most important information I should know about CONTRAVE?"
- Seizures. There is a risk of having a seizure when you take CONTRAVE. The risk of seizure is higher in people who:
  - take higher doses of CONTRAVE
  - have certain medical conditions
  - take CONTRAVE with certain other medicines
  Do not take any other medicines while you are taking CONTRAVE unless your healthcare provider has said it is okay to take them.
  If you have a seizure while taking CONTRAVE, stop taking CONTRAVE and call your healthcare provider right away.
  You should not take CONTRAVE again if you have a seizure.
- Risk of opioid overdose. One of the ingredients in CONTRAVE (naltrexone) can increase your chance of having an opioid overdose if you take opioid medicines while taking CONTRAVE.
  You can accidentally overdose in 2 ways:
  - Naltrexone blocks the effects of opioids, such as heroin, methadone or opioid pain medicines. Do not take large amounts of opioids, including opioid-containing medicines, such as heroin or prescription pain pills, to try to overcome the opioid-blocking effects of naltrexone. This can lead to serious injury, coma, or death.
  - After you take naltrexone, its blocking effect slowly decreases and completely goes away over time. If you have used opioid street drugs or opioid-containing medicines in the past, using opioids in amounts that you used before treatment with naltrexone can lead to overdose and death. You may also be more sensitive to the effects of lower amounts of opioids:
  - after you have gone through detoxification
  - when your next dose of CONTRAVE is due
  - if you miss a dose of CONTRAVE
  - after you stop CONTRAVE treatment
  It is important that you tell your family and the people closest to you of this increased sensitivity to opioids and the risk of overdose.
  You or someone close to you should get emergency medical help right away if you:

- have trouble breathing
- become very drowsy with slowed breathing
- have slow, shallow breathing (little chest movement with breathing)
- feel faint, very dizzy, confused, or have unusual symptoms

- Sudden opioid withdrawal. People who take CONTRAVE must not use any type of opioid (must be opioid-free) including street drugs, prescription pain medicines (including tramadol), cough, cold, or diarrhea medicines that contain opioids, or opioid dependence treatments, buprenorphine or methadone, for at least 7 to 10 days before starting CONTRAVE. Using opioids in the 7 to 10 days before you start taking CONTRAVE may cause you to suddenly have symptoms of opioid withdrawal when you take it. Sudden opioid withdrawal can be severe, and you may need to go to the hospital. Tell your healthcare provider you are taking CONTRAVE before a medical procedure or surgery.
- Severe allergic reactions. Some people have had a severe allergic reaction to bupropion, one of the ingredients in CONTRAVE. Stop taking CONTRAVE and call your healthcare provider or go to the nearest hospital emergency room right away if you have any of the following signs and symptoms of an allergic reaction:

- rash
- itching
- hives
- fever
- swollen lymph glands

- painful sores in your mouth or around your eyes
- swelling of your lips or tongue
- chest pain
- trouble breathing

- Increases in blood pressure or heart rate. Some people may get high blood pressure or have a higher heart rate when taking CONTRAVE. Your healthcare provider should check your blood pressure and heart rate before you start taking, and while you take CONTRAVE.
- Liver damage or hepatitis. One of the ingredients in CONTRAVE, naltrexone can cause liver damage or hepatitis. Stop taking CONTRAVE and tell your healthcare provider if you have any of the following symptoms of liver problems:
  - stomach area pain lasting more than a few days
  - dark urine
  - yellowing of the whites of your eyes
  - tiredness
  Your healthcare provider may need to stop treating you with CONTRAVE if you get signs or symptoms of a serious liver problem.
- Manic episodes. One of the ingredients in CONTRAVE, bupropion can cause some people who were manic or depressed in the past to become manic or depressed again.
- Visual problems (angle-closure glaucoma). One of the ingredients in CONTRAVE, bupropion, can cause some people to have visual problems (angle-closure glaucoma). Signs and symptoms of angle-closure glaucoma may include:
  - eye pain
  - changes in vision
  - swelling or redness in or around the eye
  Talk with your healthcare provider to find out if you are at risk for angle-closure glaucoma and to get treatment to prevent it if you are at risk.
- Increased risk of low blood sugar (hypoglycemia) in people with type 2 diabetes mellitus who also take medicines to treat their diabetes. Weight loss can cause low blood sugar in people with type 2 diabetes mellitus who also take medicines used to treat type 2 diabetes mellitus (such as insulin or sulfonylureas). You should check your blood sugar before you start taking CONTRAVE and while you take CONTRAVE.

The most common side effects of CONTRAVE include:

- nausea
- constipation
- headache
- vomiting

- dizziness
- trouble sleeping
- dry mouth
- diarrhea

These are not all of the possible side effects of CONTRAVE.

Call your doctor for medical advice about side effects. You may report side effects to FDA at 1-800-FDA-1088.

How should I store CONTRAVE?

Store CONTRAVE at room temperature between 68°F to 77°F (20°C to 25°C).

Keep CONTRAVE and all medicines out of the reach of children.

General information about the safe and effective use of CONTRAVE.

Medicines are sometimes prescribed for purposes other than those listed in a Medication Guide. Do not use CONTRAVE for a condition for which it was not prescribed. Do not give CONTRAVE to other people, even if they have the same symptoms that you have. It may harm them.

If you take a urine drug screening test, CONTRAVE may make the test result positive for amphetamines. If you tell the person giving you the drug screening test that you are taking CONTRAVE, they can do a more specific drug screening test that should not have this problem.

You can ask your pharmacist or healthcare provider for information about CONTRAVE that is written for health professionals.

What are the ingredients in CONTRAVE?

Active ingredient: naltrexone hydrochloride and bupropion hydrochloride

Inactive ingredients: microcrystalline cellulose, hydroxypropyl cellulose, lactose anhydrous, L-cysteine hydrochloride, crospovidone, magnesium stearate, hypromellose, edetate disodium, lactose monohydrate, colloidal silicon dioxide, Opadry II Blue and FD&C Blue #2 aluminum lake

Distributed by: Currax™ Pharmaceuticals LLC. Brentwood, TN 37027
CONTRAVE® is a registered trademark of Nalpropion Pharmaceuticals LLC
All other trademarks are the property of their respective owners.
© 2025 Nalpropion Pharmaceuticals LLC
For more information, go to www.contrave.com or call 1-800-793-2145.

This Medication Guide has been approved by the U.S. Food and Drug Administration

Revised: 11/2025

PRINCIPAL DISPLAY PANEL - 8 mg/90 mg Tablet Bottle Label

NDC 51267-890-99

120 tablets

Contrave®
(naltrexone HCl/bupropion HCl)
Extended-Release Tablets

8 mg/90 mg

Attention: Dispense with the
attached Medication Guide

Tablets should not be cut, chewed,
or crushed.

Currax™
pharmaceuticals LLC

Rx only